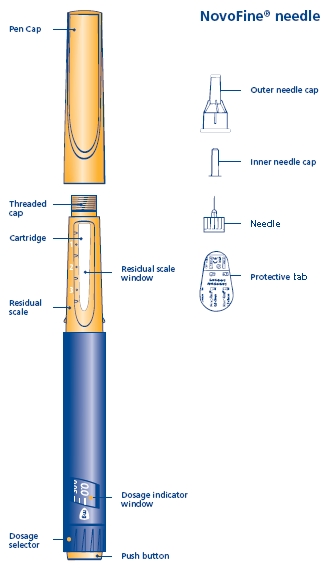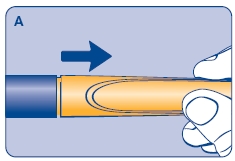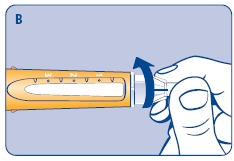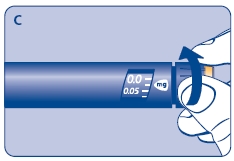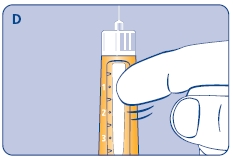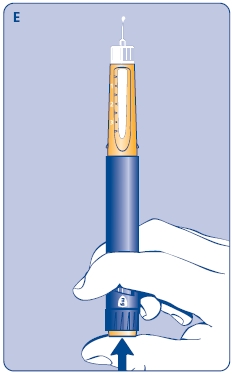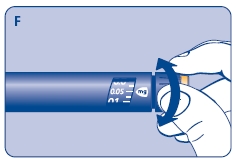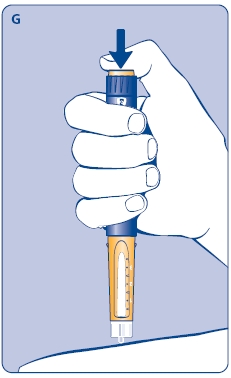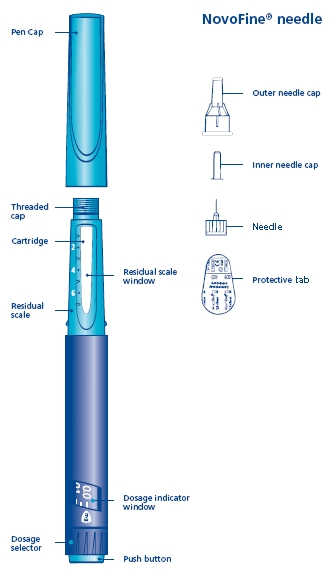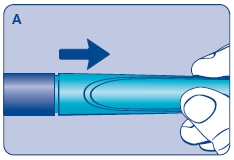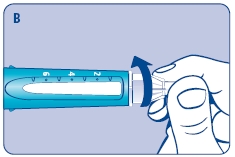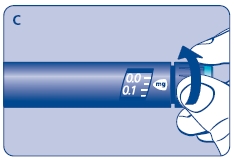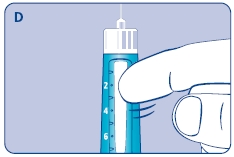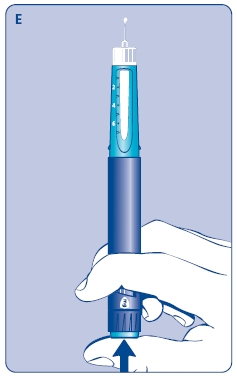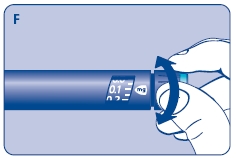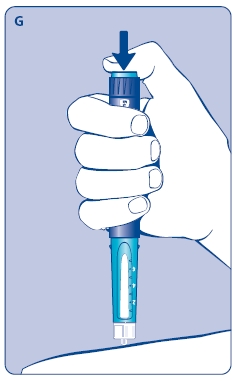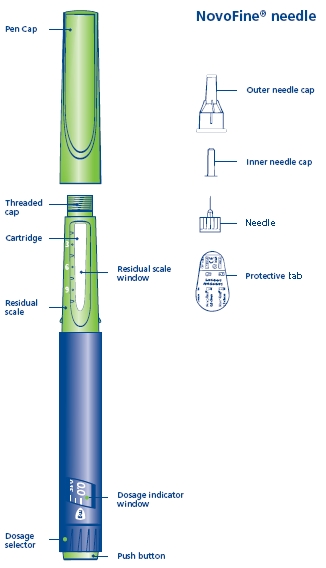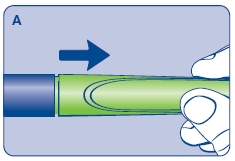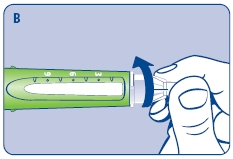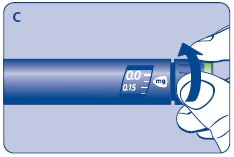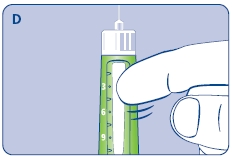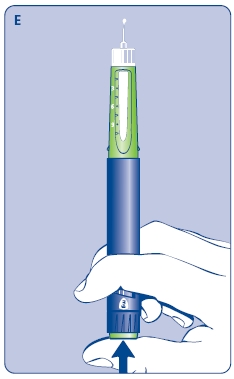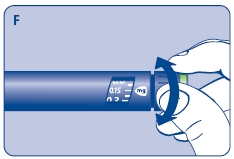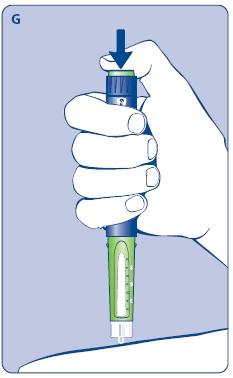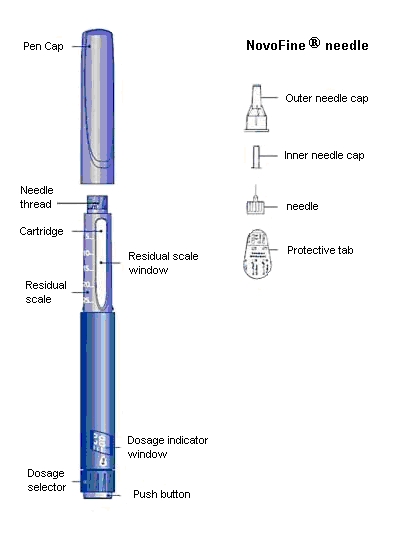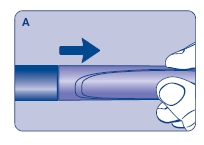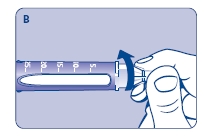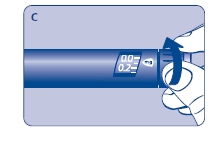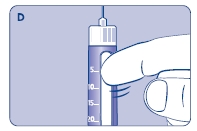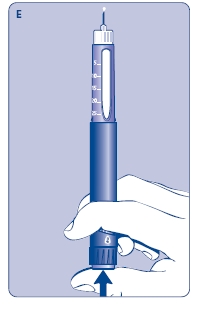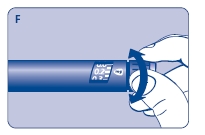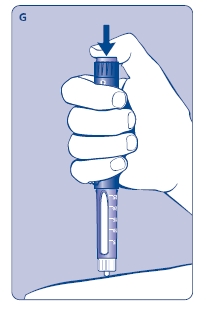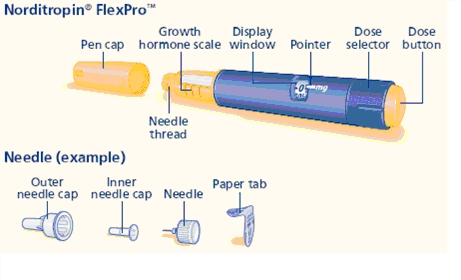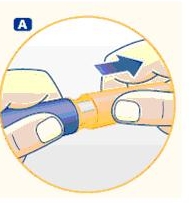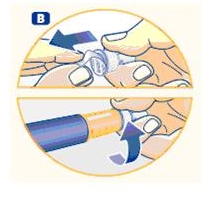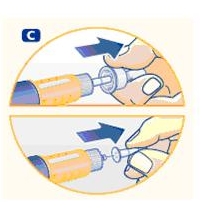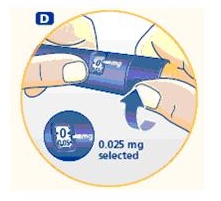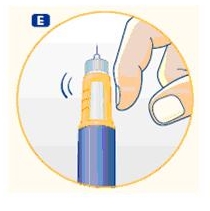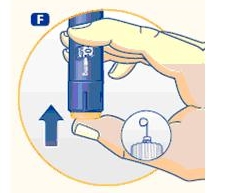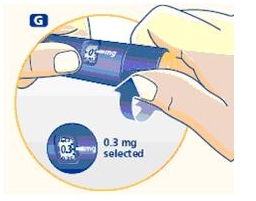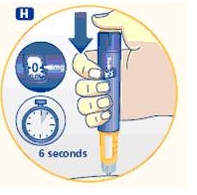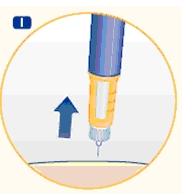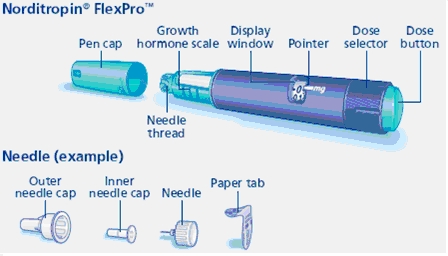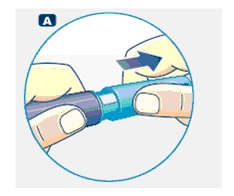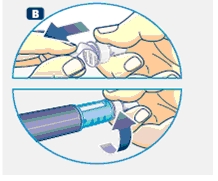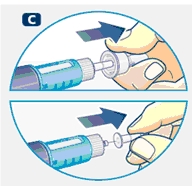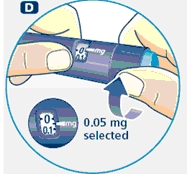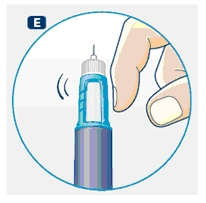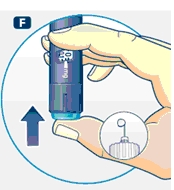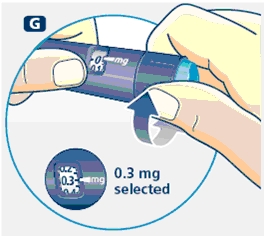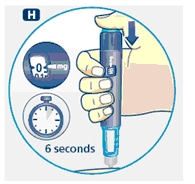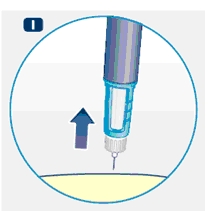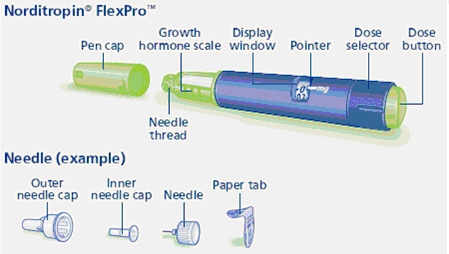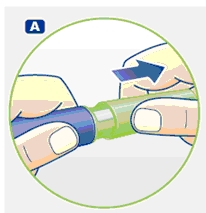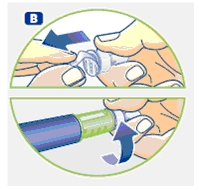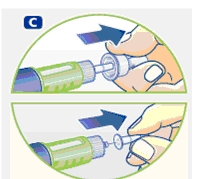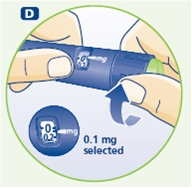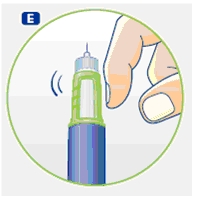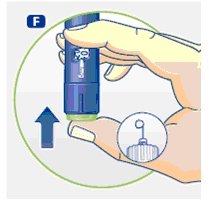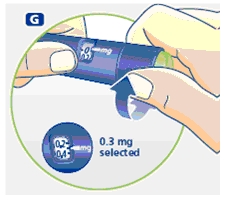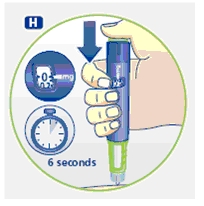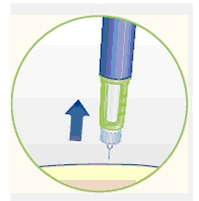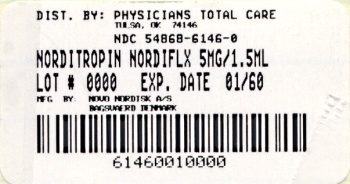 DRUG LABEL: Norditropin
NDC: 54868-6146 | Form: INJECTION, SOLUTION
Manufacturer: Physicians Total Care, Inc.
Category: prescription | Type: HUMAN PRESCRIPTION DRUG LABEL
Date: 20100302

ACTIVE INGREDIENTS: SOMATROPIN 5 mg/1.5 mL
INACTIVE INGREDIENTS: HISTIDINE 1 mg/1.5 mL; HYDROCHLORIC ACID; MANNITOL 60 mg/1.5 mL; PHENOL 4.5 mg/1.5 mL; POLOXAMER 188 4.5 mg/1.5 mL; SODIUM HYDROXIDE; WATER

HIGHLIGHTS OF PRESCRIBING INFORMATION

These highlights do not include all the information needed to use Norditropin Cartridges safely and effectively. See full prescribing information for Norditropin Cartridges.
Norditropin® Cartridges [somatropin (rDNA origin) injection], for subcutaneous use
Initial U.S. Approval: 1987

1 INDICATIONS AND USAGE

Norditropin is a recombinant human growth hormone indicated for:

- Pediatric: Treatment of children with growth failure due to growth hormone deficiency (GHD), short stature associated with Noonan syndrome, short stature associated with Turner syndrome and short stature born SGA with no catch-up growth by age 2-4 years (1.1)
- Adult: Treatment of adults with either adult onset or childhood onset GHD (1.2)

2 DOSAGE AND ADMINISTRATION

Norditropin should be administered subcutaneously (2).

- Pediatric GHD: 0.024-0.034 mg/kg/day, 6-7 times a week (2.1)
- Noonan Syndrome: Up to 0.066 mg/kg/day (2.1)
- Turner Syndrome: Up to 0.067 mg/kg/day (2.1)
- SGA: Up to 0.067 mg/kg/day (2.1)
- Adult GHD: 0.004 mg/kg/day to be increased as tolerated to not more than 0.016 mg/kg/day after approximately 6 weeks, or a starting dose of approximately 0.2 mg/day (range, 0.15-0.30 mg/day) increased gradually every 1-2 months by increments of approximately 0.1-0.2 mg/day (2.2)
- Norditropin cartridges must be used with their corresponding color-coded NordiPen delivery systems (2.3)
- Injection sites should always be rotated to avoid lipoatrophy (2.3)

3 DOSAGE FORMS AND STRENGTHS

Norditropin is preloaded in the Norditropin FlexPro or Norditropin NordiFlex pens, or cartridges for use with the corresponding NordiPens (3):

- 5 mg/1.5 mL (orange): FlexPro and NordiFlex pens, and cartridges
- 10 mg/1.5 mL (blue): FlexPro and NordiFlex pens
- 15 mg/1.5 mL (green): FlexPro and NordiFlex pens, and cartridges
- 30 mg/3 mL (purple): Norditropin NordiFlex pen only

4 CONTRAINDICATIONS

- Acute Critical Illness (4.1, 5.1)
- Children with Prader-Willi syndrome who are severely obese or have severe respiratory impairment - reports of sudden death (4.2, 5.2)
- Active Malignancy (4.3)
- Active Proliferative or Severe Non-Proliferative Diabetic Retinopathy (4.4)
- Children with closed epiphyses (4.5)
- Known hypersensitivity to somatropin or excipients (4.6)

5 WARNINGS AND PRECAUTIONS

- Acute Critical Illness: Potential benefit of treatment continuation should be weighed against the potential risk (5.1)
- Prader-Willi Syndrome in Children: Evaluate for signs of upper airway obstruction and sleep apnea before initiation of treatment for GHD. Discontinue treatment if these signs occur (5.2)
- Neoplasm: Monitor patients with preexisting tumors for progression or recurrence. Increased risk of a second neoplasm in childhood cancer survivors treated with somatropin - in particular meningiomas in patients treated with radiation to the head for their first neoplasm (5.3)
- Impaired Glucose Tolerance and Diabetes Mellitus: May be unmasked. Periodically monitor glucose levels in all patients. Doses of concurrent antihyperglycemic drugs in diabetics may require adjustment (5.4)
- Intracranial Hypertension: Exclude preexisting papilledema. May develop and is usually reversible after discontinuation or dose reduction (5.5)
- Fluid Retention (i.e., edema, arthralgia, carpal tunnel syndrome - especially in adults): May occur frequently. Reduce dose as necessary (5.6)
- Hypothyroidism: May first become evident or worsen (5.7)
- Slipped Capital Femoral Epiphysis: May develop. Evaluate children with the onset of a limp or hip/knee pain (5.8)
- Progression of Preexisting Scoliosis: May develop (5.9)

6 ADVERSE REACTIONS

Other common somatropin-related adverse reactions include injection site reactions/rashes and lipoatrophy (6.1) and headaches (6.3).

To report SUSPECTED ADVERSE REACTIONS, contact Novo Nordisk at 1-888-NOVO-444 (1-888-668-6444) or FDA at 1-800-FDA-1088, or www.fda.gov/medwatch.

7 DRUG INTERACTIONS

- Inhibition of 11ß-Hydroxysteroid Dehydrogenase Type 1: May require the initiation of glucocorticoid replacement therapy. Patients treated with glucocorticoid replacement for previously diagnosed hypoadrenalism may require an increase in their maintenance doses (7.1)
- Glucocorticoid Replacement: Should be carefully adjusted (7.2)
- Cytochrome P450-Metabolized Drugs: Monitor carefully if used with somatropin (7.3)
- Oral Estrogen: Larger doses of somatropin may be required in women (7.4)
- Insulin and/or Oral Hypoglycemic Agents: May require adjustment (7.5)

FULL PRESCRIBING INFORMATION

1 INDICATIONS AND USAGE

1.1 Pediatric Patients

Norditropin [somatropin (rDNA origin) injection] is indicated for the treatment of children with growth failure due to inadequate secretion of endogenous growth hormone (GH).

Norditropin [somatropin (rDNA origin) injection] is indicated for the treatment of children with short stature associated with Noonan syndrome.

Norditropin [somatropin (rDNA origin) injection] is indicated for the treatment of children with short stature associated with Turner syndrome.

Norditropin [somatropin (rDNA origin) injection] is indicated for the treatment of children with short stature born small for gestational age (SGA) with no catch-up growth by age 2-4 years.

1.2 Adult Patients

Norditropin [somatropin (rDNA origin) injection] is indicated for the replacement of endogenous GH in adults with growth hormone deficiency (GHD) who meet either of the following two criteria:

- Adult Onset (AO): Patients who have GHD, either alone or associated with multiple hormone deficiencies (hypopituitarism), as a result of pituitary disease, hypothalamic disease, surgery, radiation therapy, or trauma; or
- Childhood Onset (CO): Patients who were GH deficient during childhood as a result of congenital, genetic, acquired, or idiopathic causes.

Patients who were treated with somatropin for GHD in childhood and whose epiphyses are closed should be reevaluated before continuation of somatropin therapy at the reduced dose level recommended for GHD adults. According to current standards, confirmation of the diagnosis of adult GHD in both groups involves an appropriate growth hormone provocative test with two exceptions: (1) patients with multiple other pituitary hormone deficiencies due to organic disease; and (2) patients with congenital/genetic growth hormone deficiency.

2 DOSAGE AND ADMINISTRATION

For subcutaneous injection.

Therapy with Norditropin should be supervised by a physician who is experienced in the diagnosis and management of pediatric patients with short stature associated with GHD, Noonan syndrome, Turner syndrome or SGA, and adult patients with either childhood onset or adult onset GHD.

2.1 Dosing of Pediatric Patients

General Pediatric Dosing Information

The Norditropin dosage and administration schedule should be individualized based on the growth response of each patient. Serum insulin-like growth factor I (IGF-I) levels may be useful during dose titration.

Response to somatropin therapy in pediatric patients tends to decrease with time. However, in pediatric patients, the failure to increase growth rate, particularly during the first year of therapy, indicates the need for close assessment of compliance and evaluation for other causes of growth failure, such as hypothyroidism, undernutrition, advanced bone age and antibodies to recombinant human GH (rhGH).

Treatment with Norditropin for short stature should be discontinued when the epiphyses are fused.

Pediatric Growth Hormone Deficiency (GHD)

A dosage of 0.024 - 0.034 mg/kg/day, 6-7 times a week, is recommended.

Pediatric Patients with Short Stature Associated with Noonan Syndrome

Not all patients with Noonan syndrome have short stature; some will achieve a normal adult height without treatment. Therefore, prior to initiating Norditropin for a patient with Noonan syndrome, establish that the patient does have short stature.

A dosage of up to 0.066 mg/kg/day is recommended.

Pediatric Patients with Short Stature Associated with Turner Syndrome

A dosage of up to 0.067 mg/kg/day is recommended.

Pediatric Patients with Short Stature Born Small for Gestational Age (SGA) with No Catch-up Growth by Age 2-4 Years

A dosage of up to 0.067 mg/kg/day is recommended.

Recent literature has recommended initial treatment with larger doses of somatropin (e.g., 0.067 mg/kg/day), especially in very short children (i.e., HSDS < -3), and/or older/pubertal children, and that a reduction in dosage (e.g., gradually towards 0.033 mg/kg/day) should be considered if substantial catch-up growth is observed during the first few years of therapy. On the other hand, in younger SGA children (e.g., approximately < 4 years) (who respond the best in general) with less severe short stature (i.e., baseline HSDS values between -2 and -3), consideration should be given to initiating treatment at a lower dose (e.g., 0.033 mg/kg/day), and titrating the dose as needed over time. In all children, clinicians should carefully monitor the growth response, and adjust the rhGH dose as necessary.

2.2 Dosing of Adult Patients

Adult Growth Hormone Deficiency (GHD)

Either of two approaches to Norditropin dosing may be followed: a non-weight-based regimen or a weight-based regimen.

Non-weight based — based on published consensus guidelines, a starting dose of approximately 0.2 mg/day (range, 0.15-0.30 mg/day) may be used without consideration of body weight. This dose can be increased gradually every 1-2 months by increments of approximately 0.1-0.2 mg/day, according to individual patient requirements based on the clinical response and serum insulin-like growth factor I (IGF-I) concentrations. The dose should be decreased as necessary on the basis of adverse events and/or serum IGF-I concentrations above the age- and gender-specific normal range. Maintenance dosages vary considerably from person to person, and between male and female patients.

Weight-based — based on the dosing regimen used in the original adult GHD registration trials, the recommended dosage at the start of treatment is not more than 0.004 mg/kg/day. The dose may be increased to not more than 0.016 mg/kg/day after approximately 6 weeks according to individual patient requirements. Clinical response, side effects, and determination of age- and gender-adjusted serum IGF-I concentrations should be used as guidance in dose titration.

A lower starting dose and smaller dose increments should be considered for older patients, who are more prone to the adverse effects of somatropin than younger individuals. In addition, obese individuals are more likely to manifest adverse effects when treated with a weight-based regimen. In order to reach the defined treatment goal, estrogen-replete women may need higher doses than men. Oral estrogen administration may increase the dose requirements in women.

2.3 Preparation and Administration

Norditropin® FlexPro® 5 mg/ 1.5 mL, 10 mg/1.5 mL and 15 mg/1.5 mL:

Instructions for delivering the dosage are provided in the PATIENT INFORMATION and INSTRUCTIONS FOR USE leaflets enclosed with the Norditropin FlexPro prefilled pen.

Norditropin NordiFlex® 5 mg/1.5 mL, 10 mg/1.5 mL, 15 mg/1.5 mL and 30 mg/3 mL:

Instructions for delivering the dosage are provided in the PATIENT INFORMATION and INSTRUCTIONS FOR USE leaflets enclosed with the Norditropin NordiFlex prefilled pen.

Norditropin Cartridges must be administered using the NordiPen delivery systems. Each cartridge size has a corresponding, color-coded pen which is graduated to deliver the appropriate dose based on the concentration of Norditropin in the cartridge.

Norditropin® Cartridges 5 mg/1.5 mL and 15 mg/1.5 mL:

Each cartridge of Norditropin must be inserted into its corresponding NordiPen delivery system. Instructions for delivering the dosage are provided in the NordiPen INSTRUCTION booklet.

Parenteral drug products should always be inspected visually for particulate matter and discoloration prior to administration, whenever solution and container permit. Norditropin MUST NOT BE INJECTED if the solution is cloudy or contains particulate matter. Use it only if it is clear and colorless.

Injection sites should always be rotated to avoid lipoatrophy.

3 DOSAGE FORMS AND STRENGTHS

Norditropin is available preloaded in the Norditropin FlexPro or Norditropin NordiFlex pens or in cartridges for use with the corresponding NordiPens:

- 5 mg/1.5 mL (orange): Norditropin FlexPro and Norditropin NordiFlex prefilled pens, and cartridges
- 10 mg/1.5 mL (blue): Norditropin FlexPro and Norditropin NordiFlex prefilled pens
- 15 mg/1.5 mL (green): Norditropin FlexPro and Norditropin NordiFlex prefilled pens, and cartridges
- 30 mg/3 mL (purple): Norditropin NordiFlex prefilled pen only

4 CONTRAINDICATIONS

4.1 Acute Critical Illness

Treatment with pharmacologic amounts of somatropin is contraindicated in patients with acute critical illness due to complications following open heart surgery, abdominal surgery or multiple accidental trauma, or those with acute respiratory failure. Two placebo-controlled clinical trials in non-growth hormone deficient adult patients (n=522) with these conditions in intensive care units revealed a significant increase in mortality (41.9% vs. 19.3%) among somatropin-treated patients (doses 5.3-8 mg/day) compared to those receiving placebo [see Warnings and Precautions (5.1)].

4.2 Prader-Willi Syndrome in Children

Somatropin is contraindicated in patients with Prader-Willi syndrome who are severely obese, have a history of upper airway obstruction or sleep apnea, or have severe respiratory impairment [see Warnings and Precautions (5.2)]. There have been reports of sudden death when somatropin was used in such patients [see Warnings and Precautions (5.2)]. Norditropin is not indicated for the treatment of pediatric patients who have growth failure due to genetically confirmed Prader-Willi syndrome.

4.3 Active Malignancy

In general, somatropin is contraindicated in the presence of active malignancy. Any preexisting malignancy should be inactive and its treatment complete prior to instituting therapy with somatropin. Somatropin should be discontinued if there is evidence of recurrent activity. Since GHD may be an early sign of the presence of a pituitary tumor (or, rarely, other brain tumors), the presence of such tumors should be ruled out prior to initiation of treatment. Somatropin should not be used in patients with any evidence of progression or recurrence of an underlying intracranial tumor.

4.4 Diabetic Retinopathy

Somatropin is contraindicated in patients with active proliferative or severe non-proliferative diabetic retinopathy.

4.5 Closed Epiphyses

Somatropin should not be used for growth promotion in pediatric patients with closed epiphyses.

4.6 Hypersensitivity

Norditropin is contraindicated in patients with a known hypersensitivity to somatropin or any of its excipients. Localized reactions are the most common hypersensitivity reactions.

5 WARNINGS AND PRECAUTIONS

5.1 Acute Critical Illness

Increased mortality in patients with acute critical illness due to complications following open heart surgery, abdominal surgery or multiple accidental trauma, or those with acute respiratory failure has been reported after treatment with pharmacologic amounts of somatropin [see Contraindications (4.1)]. The safety of continuing somatropin treatment in patients receiving replacement doses for approved indications who concurrently develop these illnesses has not been established. Therefore, the potential benefit of treatment continuation with somatropin in patients experiencing acute critical illnesses should be weighed against the potential risk.

5.2 Prader-Willi Syndrome in Children

There have been reports of fatalities after initiating therapy with somatropin in pediatric patients with Prader-Willi syndrome who had one or more of the following risk factors: severe obesity, history of upper airway obstruction or sleep apnea, or unidentified respiratory infection. Male patients with one or more of these factors may be at greater risk than females. Patients with Prader-Willi syndrome should be evaluated for signs of upper airway obstruction and sleep apnea before initiation of treatment with somatropin. If, during treatment with somatropin, patients show signs of upper airway obstruction (including onset of or increased snoring) and/or new onset sleep apnea, treatment should be interrupted. All patients with Prader-Willi syndrome treated with somatropin should also have effective weight control and be monitored for signs of respiratory infection, which should be diagnosed as early as possible and treated aggressively [see Contraindications (4.2)]. Norditropin is not indicated for the treatment of pediatric patients who have growth failure due to genetically confirmed Prader-Willi syndrome.

5.3 Neoplasms

Patients with preexisting tumors or GHD secondary to an intracranial lesion should be monitored routinely for progression or recurrence of the underlying disease process. In pediatric patients, clinical literature has revealed no relationship between somatropin replacement therapy and central nervous system (CNS) tumor recurrence or new extracranial tumors. However, in childhood cancer survivors, an increased risk of a second neoplasm has been reported in patients treated with somatropin after their first neoplasm. Intracranial tumors, in particular meningiomas, in patients treated with radiation to the head for their first neoplasm, were the most common of these second neoplasms. In adults, it is unknown whether there is any relationship between somatropin replacement therapy and CNS tumor recurrence.

Patients should be monitored carefully for potential malignant transformation of skin lesions, i.e. increased growth of preexisting nevi.

5.4 Glucose Intolerance

Treatment with somatropin may decrease insulin sensitivity, particularly at higher doses in susceptible patients. As a result, previously undiagnosed impaired glucose tolerance and overt diabetes mellitus may be unmasked during somatropin treatment. Therefore, glucose levels should be monitored periodically in all patients treated with somatropin, especially in those with risk factors for diabetes mellitus, such as obesity, Turner syndrome, or a family history of diabetes mellitus. Patients with preexisting type 1 or type 2 diabetes mellitus or impaired glucose tolerance should be monitored closely during somatropin therapy. The doses of antihyperglycemic drugs (i.e., insulin or oral agents) may require adjustment when somatropin therapy is instituted in these patients.

5.5 Intracranial Hypertension

Intracranial hypertension (IH) with papilledema, visual changes, headache, nausea, and/or vomiting has been reported in a small number of patients treated with somatropin products. Symptoms usually occurred within the first eight (8) weeks after the initiation of somatropin therapy. In all reported cases, IH-associated signs and symptoms rapidly resolved after cessation of therapy or a reduction of the somatropin dose.

Funduscopic examination should be performed routinely before initiating treatment with somatropin to exclude preexisting papilledema, and periodically during the course of somatropin therapy. If papilledema is observed by funduscopy during somatropin treatment, treatment should be stopped. If somatropin-induced IH is diagnosed, treatment with somatropin can be restarted at a lower dose after IH-associated signs and symptoms have resolved. Patients with Turner syndrome may be at increased risk for the development of IH.

5.6 Fluid Retention

Fluid retention during somatropin replacement therapy in adults may frequently occur. Clinical manifestations of fluid retention are usually transient and dose dependent.

5.7 Hypothyroidism

Undiagnosed/untreated hypothyroidism may prevent an optimal response to somatropin, in particular, the growth response in children. Patients with Turner syndrome have an inherently increased risk of developing autoimmune thyroid disease and primary hypothyroidism. In patients with GHD, central (secondary) hypothyroidism may first become evident or worsen during somatropin treatment. Therefore, patients treated with somatropin should have periodic thyroid function tests and thyroid hormone replacement therapy should be initiated or appropriately adjusted when indicated.

In patients with hypopituitarism (multiple hormone deficiencies), standard hormonal replacement therapy should be monitored closely when somatropin therapy is administered.

5.8 Slipped Capital Femoral Epiphysis in Pediatric Patients

Slipped capital femoral epiphysis may occur more frequently in patients with endocrine disorders (including GHD and Turner syndrome) or in patients undergoing rapid growth. Any pediatric patient with the onset of a limp or complaints of hip or knee pain during somatropin therapy should be carefully evaluated.

5.9 Progression of Preexisting Scoliosis in Pediatric Patients

Progression of scoliosis can occur in patients who experience rapid growth. Because somatropin increases growth rate, patients with a history of scoliosis who are treated with somatropin should be monitored for progression of scoliosis. However, somatropin has not been shown to increase the occurrence of scoliosis. Skeletal abnormalities including scoliosis are commonly seen in untreated patients with Turner syndrome and Noonan syndrome. Scoliosis is also commonly seen in untreated patients with Prader-Willi syndrome. Physicians should be alert to these abnormalities, which may manifest during somatropin therapy.

5.10 Otitis Media and Cardiovascular Disorders in Turner Syndrome

Patients with Turner syndrome should be evaluated carefully for otitis media and other ear disorders since these patients have an increased risk of ear and hearing disorders. Somatropin treatment may increase the occurrence of otitis media in patients with Turner syndrome. In addition, patients with Turner syndrome should be monitored closely for cardiovascular disorders (e.g., stroke, aortic aneurysm/dissection, hypertension) as these patients are also at risk for these conditions.

5.11 Confirmation of Childhood Onset Adult GHD

Patients with epiphyseal closure who were treated with somatropin replacement therapy in childhood should be reevaluated according to the criteria in Indications and Usage (1.2) before continuation of somatropin therapy at the reduced dose level recommended for GH deficient adults.

5.12 Local and Systemic Reactions

When somatropin is administered subcutaneously at the same site over a long period of time, tissue atrophy may result. This can be avoided by rotating the injection site [see Dosage and Administration (2.3)].

As with any protein, local or systemic allergic reactions may occur. Parents/Patients should be informed that such reactions are possible and that prompt medical attention should be sought if allergic reactions occur.

5.13 Laboratory Tests

Serum levels of inorganic phosphorus, alkaline phosphatase, parathyroid hormone (PTH) and IGF-I may increase after somatropin therapy.

6 ADVERSE REACTIONS

6.1 Most Serious and/or Most Frequently Observed Adverse Reactions

This list presents the most seriousb and/or most frequently observeda adverse reactions during treatment with somatropin:

- bSudden death in pediatric patients with Prader-Willi syndrome with risk factors including severe obesity, history of upper airway obstruction or sleep apnea and unidentified respiratory infection [see Contraindications (4.2) and Warnings and Precautions (5.2)]
- bIntracranial tumors, in particular meningiomas, in teenagers/young adults treated with radiation to the head as children for a first neoplasm and somatropin [see Contraindications (4.3) and Warnings and Precautions (5.3)]
- a,bGlucose intolerance including impaired glucose tolerance/impaired fasting glucose as well as overt diabetes mellitus [see Warnings and Precautions (5.4)]
- bIntracranial hypertension [see Warnings and Precautions (5.5)]
- bSignificant diabetic retinopathy [see Contraindications (4.4)]
- bSlipped capital femoral epiphysis in pediatric patients [see Warnings and Precautions (5.8)]
- bProgression of preexisting scoliosis in pediatric patients [see Warnings and Precautions (5.9)]
- aFluid retention manifested by edema, arthralgia, myalgia, nerve compression syndromes including carpal tunnel syndrome/paraesthesias [see Warnings and Precautions (5.6)]
- aUnmasking of latent central hypothyroidism [see Warnings and Precautions (5.7)]
- aInjection site reactions/rashes and lipoatrophy (as well as rare generalized hypersensitivity reactions) [see Warnings and Precautions (5.12)]

6.2 Clinical Trials Experience

Because clinical trials are conducted under varying conditions, adverse reaction rates observed during the clinical trials performed with one somatropin formulation cannot always be directly compared to the rates observed during the clinical trials performed with a second somatropin formulation, and may not reflect the adverse reaction rates observed in practice.

Clinical Trials in Pediatric GHD Patients

As with all protein drugs, a small percentage of patients may develop antibodies to the protein. GH antibodies with binding capacities lower than 2 mg/L have not been associated with growth attenuation. In a very small number of patients, when binding capacity was greater than 2 mg/L, interference with the growth response was observed. In clinical trials, patients receiving Norditropin for up to 12 months were tested for induction of antibodies, and 0/358 patients developed antibodies with binding capacities above 2 mg/L. Amongst these patients, 165 had previously been treated with other somatropin formulations, and 193 were previously untreated naive patients.

Clinical Trials in Children with Noonan Syndrome

Norditropin was studied in a two-year prospective, randomized, parallel dose group trial in 21 children, 3-14 years old, with Noonan syndrome. Doses were 0.033 and 0.066 mg/kg/day. After the initial two-year randomized trial, children continued Norditropin treatment until final height was achieved; randomized dose groups were not maintained. Final height and adverse event data were later collected retrospectively from 18 children; total follow-up was 11 years. An additional 6 children were not randomized, but followed the protocol and are included in this assessment of adverse events.

Based on the mean dose per treatment group, no significant difference in the incidence of adverse events was seen between the two groups. The most frequent adverse events were the common infections of childhood, including upper respiratory infection, gastroenteritis, ear infection, and influenza. Cardiac disorders was the system organ class with the second most adverse events reported. However, congenital heart disease is an inherent component of Noonan syndrome, and there was no evidence of somatropin-induced ventricular hypertrophy or exacerbation of preexisting ventricular hypertrophy (as judged by echocardiography) during this study. Children who had baseline cardiac disease judged to be significant enough to potentially affect growth were excluded from the study; therefore the safety of Norditropin in children with Noonan syndrome and significant cardiac disease is not known. Among children who received 0.033 mg/kg/day, there was one adverse event of scoliosis; among children who received 0.066 mg/kg/day, there were four adverse events of scoliosis [see Warnings and Precautions (5.9)]. Mean serum IGF-I standard deviation score (SDS) levels did not exceed +1 in response to somatropin treatment. The mean serum IGF-I level was low at baseline and normalized during treatment.

Clinical Trials in Children with Turner Syndrome

In two clinical studies wherein children with Turner syndrome were treated until final height with various doses of Norditropin as described in Clinical Studies (14.2), the most frequently reported adverse events were common childhood diseases including influenza-like illness, otitis media, upper respiratory tract infection, otitis externa, gastroenteritis and eczema. Otitis media adverse events in Study 1 were most frequent in the highest dose groups (86.4% in the 0.045-0.067-0.089 mg/kg/day group vs. 78.3% in the 0.045-0.067 mg/kg/day group vs. 69.6% in the 0.045 mg/kg/day group) suggesting a possible dose-response relationship. Of note, approximately 40-50% of these otitis media adverse events were designated as “serious” [see Warnings and Precautions (5.10)]. No patients in either study developed clearcut overt diabetes mellitus; however, in Study 1, impaired fasting glucose at Month 48 was more frequent in patients in the 0.045-0.067 mg/kg/day group (n=4/18) compared with the 0.045 mg/kg/day group (n=1/20). Transient episodes of fasting blood sugars between 100 and 126 mg/dL, and, on occasion, exceeding 126 mg/dL also occurred more often with larger doses of Norditropin in both studies [see Warnings and Precautions (5.4) and Adverse Reactions (6.1)]. Three patients withdrew from the 2 high dose groups in Study 1 because of concern about excessive growth of hands or feet. In addition, in Study 1, exacerbation of preexisting scoliosis was designated a serious adverse reaction in two patients in the 0.045 mg/kg/day group [see Warnings and Precautions (5.9)].

Clinical Trials in Children Born Small for Gestational Age (SGA) with No Catch-up Growth by Age 2-4 Years

Study 1 (Long-Term)

In a multi-center, randomized, double-blind study, 53 non-GHD children with short stature born SGA with failure to catch-up were treated with 2 doses of Norditropin (0.033 or 0.067 mg/kg/day) to final height for up to 13 years (mean duration of treatment 7.9 and 9.5 years for girls and boys, respectively). The most frequently reported adverse events were common childhood diseases including influenza-like illness, upper respiratory tract infection, bronchitis, gastroenteritis, abdominal pain, otitis media, pharyngitis, arthralgia, and headache. Adverse events possibly/probably related to Norditropin were otitis media, arthralgia, headaches (no confirmed diagnoses of benign intracranial hypertension), gynecomastia, and increased sweating. One child treated with 0.067 mg/kg/day for 4 years was reported with disproportionate growth of the lower jaw, and another child treated with 0.067 mg/kg/day developed a melanocytic nevus [see Warnings and Precautions (5.3)]. There were no clear cut reports of exacerbation of preexisting scoliosis or slipped capital femoral epiphysis. No apparent differences between the treatment groups were observed. In addition, the timing of puberty was age-appropriate in boys and girls in both treatment groups. Therefore, it can be concluded that no novel adverse events potentially related to treatment with Norditropin were reported in long-term Study 1.

Study 2 (Short-Term)

In a multi-center, randomized, double-blind, parallel-group study, 98 Japanese non-GHD children with short stature born SGA with failure to catch-up were treated with 2 doses of Norditropin (0.033 or 0.067 mg/kg/day) for 2 years or were untreated for 1 year. The most frequently reported adverse events were common childhood diseases almost identical to those reported above for Study 1. Adverse events possibly/probably related to Norditropin were otitis media, arthralgia and impaired glucose tolerance. No apparent differences between the treatment groups were observed. However, arthralgia and transiently impaired glucose tolerance were only reported in the 0.067 mg/kg/day treatment group. Therefore, it can also be concluded that no novel adverse events potentially related to treatment with rhGH were reported in short-term Study 2.

As with all protein drugs, some patients may develop antibodies to the protein. Eighteen of the 76 children (~24%) treated with Norditropin developed anti-rhGH antibodies. However, these antibodies did not appear to be neutralizing in that the change from baseline in height SDS at Year 2 was similar in antibody positive and antibody negative children by treatment group.

In both Study 1 and Study 2, there were no clear cut cases of new onset diabetes mellitus, no children treated for hyperglycemia, and no adverse event withdrawals due to abnormalities in glucose tolerance. In Study 2, after treatment with either dose of Norditropin for 2 years, there were no children with consecutive fasting blood glucose levels between 100 and 126 mg/dL, or with fasting blood glucose levels > 126 mg/dL. Furthermore, mean hemoglobin A1c levels tended to decrease during long-term treatment in Study 1, and remained normal in Study 2. However, in Study 1, 4 children treated with 0.067 mg/kg/day of Norditropin and 2 children treated with 0.033 mg/kg/day of Norditropin shifted from normal fasting blood glucose levels at baseline to increased levels after 1 year of treatment (100 to 126 mg/dL or > 126 mg/dL). In addition, small increases in mean fasting blood glucose and insulin levels (within the normal reference range) after 1 and 2 years of Norditropin treatment appeared to be dose-dependent [see Warnings and Precautions (5.4) and Adverse Reactions (6.1)].

In both Study 1 and Study 2, there was no acceleration of bone maturation. A dose-dependent increase in mean serum IGF-I SDS levels within the reference range (but including a substantial number of children with serum IGF-1 SDS > +2) was observed after both long-term (Study 1) and short-term (Study 2) Norditropin treatment.

Clinical Trials in Adult GHD Patients

Adverse events with an incidence of ≥5% occurring in patients with AO GHD during the 6 month placebo-controlled portion of the largest of the six adult GHD Norditropin trials are presented in Table 1. Peripheral edema, other types of edema, arthralgia, myalgia, and paraesthesia were common in the Norditropin-treated patients, and reported much more frequently than in the placebo group. These types of adverse events are thought to be related to the fluid accumulating effects of somatropin. In general, these adverse events were mild and transient in nature. During the placebo-controlled portion of this study, approximately 5% of patients without preexisting diabetes mellitus treated with Norditropin were diagnosed with overt type 2 diabetes mellitus compared with none in the placebo group [see Warnings and Precautions (5.4) and Adverse Reactions (6.1)]. Anti-GH antibodies were not detected.

Of note, the doses of Norditropin employed during this study (completed in the mid 1990s) were substantially larger than those currently recommended by the Growth Hormone Research Society, and, more than likely, resulted in a greater than expected incidence of fluid retention- and glucose intolerance-related adverse events. A similar incidence and pattern of adverse events were observed during the other three placebo-controlled AO GHD trials and during the two placebo-controlled CO GHD trials.

Table 1 - Adverse Reactions with ≥5% Overall Incidence in Adult Onset Growth Hormone Deficient Patients Treated with Norditropin During a Six Month Placebo-Controlled Clinical Trial
 | Norditropin; (N=53) |  | Placebo; (N=52)
Adverse Reactions | n | % | n | %
Peripheral Edema | 22 | 42 | 4 | 8
Edema | 13 | 25 | 0 | 0
Arthralgia | 10 | 19 | 8 | 15
Leg Edema | 8 | 15 | 2 | 4
Myalgia | 8 | 15 | 4 | 8
Infection (non-viral) | 7 | 13 | 4 | 8
Paraesthesia | 6 | 11 | 3 | 6
Skeletal Pain | 6 | 11 | 1 | 2
Headache | 5 | 9 | 3 | 6
Bronchitis | 5 | 9 | 0 | 0
Flu-like symptoms | 4 | 8 | 2 | 4
Hypertension | 4 | 8 | 1 | 2
Gastroenteritis | 4 | 8 | 4 | 8
Other Non-Classifiable Disorders (excludes accidental injury) | 4 | 8 | 3 | 6
Increased sweating | 4 | 8 | 1 | 2
Glucose tolerance abnormal | 3 | 6 | 1 | 2
Laryngitis | 3 | 6 | 3 | 6

The adverse event pattern observed during the open label phase of the study was similar to the one presented above.

6.3 Post-Marketing Surveillance

Because these adverse events are reported voluntarily from a population of uncertain size, it is not always possible to reliably estimate their frequency or establish a causal relationship to drug exposure. The adverse events reported during post-marketing surveillance do not differ from those listed/discussed above in Sections 6.1 and 6.2 in children and adults.

Leukemia has been reported in a small number of GH deficient children treated with somatropin, somatrem (methionylated rhGH) and GH of pituitary origin. It is uncertain whether these cases of leukemia are related to GH therapy, the pathology of GHD itself, or other associated treatments such as radiation therapy. On the basis of current evidence, experts have not been able to conclude that GH therapy per se was responsible for these cases of leukemia. The risk for children with GHD, if any, remains to be established [see Contraindications (4.3) and Warnings and Precautions (5.3)].

The following additional adverse reactions have been observed during the appropriate use of somatropin: headaches (children and adults), gynecomastia (children), and pancreatitis (children).

7 DRUG INTERACTIONS

7.1 Inhibition of 11ß-Hydroxysteroid Dehydrogenase Type 1 (11ßHSD-1)

The microsomal enzyme 11ß-hydroxysteroid dehydrogenase type 1 (11βHSD-1) is required for conversion of cortisone to its active metabolite, cortisol, in hepatic and adipose tissue. GH and somatropin inhibit 11βHSD-1. Consequently, individuals with untreated GHD have relative increases in 11βHSD-1 and serum cortisol. Introduction of somatropin treatment may result in inhibition of 11βHSD-1 and reduced serum cortisol concentrations. As a consequence, previously undiagnosed central (secondary) hypoadrenalism may be unmasked and glucocorticoid replacement may be required in patients treated with somatropin. In addition, patients treated with glucocorticoid replacement for previously diagnosed hypoadrenalism may require an increase in their maintenance or stress doses following initiation of somatropin treatment; this may be especially true for patients treated with cortisone acetate and prednisone since conversion of these drugs to their biologically active metabolites is dependent on the activity of 11ßHSD-1.

7.2 Physiologic Glucocorticoid Replacement and Pharmacologic Glucocorticoid Therapy

Pharmacologic glucocorticoid therapy and supraphysiologic glucocorticoid treatment may attenuate the growth promoting effects of somatropin in children. Therefore, glucocorticoid replacement dosing should be carefully adjusted in children receiving concomitant somatropin and glucocorticoid treatments to avoid both hypoadrenalism and an inhibitory effect on growth.

7.3 Cytochrome P450-Metabolized Drugs

Limited published data indicate that somatropin treatment increases cytochrome P450 (CYP450)- mediated antipyrine clearance in man. These data suggest that somatropin administration may alter the clearance of compounds known to be metabolized by CYP450 liver enzymes (e.g., corticosteroids, sex steroids, anticonvulsants, cyclosporine). Careful monitoring is advisable when somatropin is administered in combination with other drugs known to be metabolized by CYP450 liver enzymes. However, formal drug interaction studies have not been conducted.

7.4 Oral Estrogen

In adult women on oral estrogen replacement, a larger dose of somatropin may be required to achieve the defined treatment goal [see Dosage and Administration (2.2)].

7.5 Insulin and/or Oral Hypoglycemic Agents

In patients with diabetes mellitus requiring drug therapy, the dose of insulin and/or oral agent may require adjustment when somatropin therapy is initiated [see Warnings and Precautions (5.4)].

8 USE IN SPECIFIC POPULATIONS

8.1 Pregnancy

Pregnancy Category C. Animal reproduction studies have not been conducted with Norditropin. It is not known whether Norditropin can cause fetal harm when administered to a pregnant woman or can affect reproductive capacity. Norditropin should be given to a pregnant woman only if clearly needed.

8.3 Nursing Mothers

It is not known whether Norditropin is excreted in human milk. Because many drugs are excreted in human milk, caution should be exercised when Norditropin is administered to a nursing woman.

8.5 Geriatric Use

The safety and effectiveness of Norditropin in patients aged 65 and over has not been evaluated in clinical studies. Elderly patients may be more sensitive to the action of somatropin, and therefore may be more prone to develop adverse reactions. A lower starting dose and smaller dose increments should be considered for older patients [see Dosage and Administration (2.2)].

10 OVERDOSAGE

Short-Term

Short-term overdosage could lead initially to hypoglycemia and subsequently to hyperglycemia. Furthermore, overdose with somatropin is likely to cause fluid retention.

Long-Term

Long-term overdosage could result in signs and symptoms of gigantism and/or acromegaly consistent with the known effects of excess growth hormone [see Dosage and Administration (2)].

11 DESCRIPTION

Norditropin is a registered trademark of Novo Nordisk Health Care AG for somatropin, a polypeptide hormone of recombinant DNA origin. The hormone is synthesized by a special strain of E. coli bacteria that has been modified by the addition of a plasmid which carries the gene for human growth hormone. Norditropin contains the identical sequence of 191 amino acids constituting the naturally occurring pituitary human growth hormone with a molecular weight of about 22,000 Daltons.

Norditropin cartridges are supplied as sterile solutions for subcutaneous injection in ready-to-administer cartridges or prefilled pens with a volume of 1.5 mL or 3 mL.

Each Norditropin Cartridge contains the following (see Table 2):

Table 2
Component | 5 mg/1.5 mL | 10 mg/1.5 mL | 15 mg/1.5 mL | 30 mg/3 mL
Somatropin | 5 mg | 10 mg | 15 mg | 30 mg
Histidine | 1 mg | 1 mg | 1.7 mg | 3.3 mg
Poloxamer 188 | 4.5 mg | 4.5 mg | 4.5 mg | 9.0 mg
Phenol | 4.5 mg | 4.5 mg | 4.5 mg | 9.0 mg
Mannitol | 60 mg | 60 mg | 58 mg | 117 mg
HCl/NaOH | as needed | as needed | as needed | as needed
Water for Injection | up to 1.5 mL | up to 1.5 mL | up to 1.5 mL | up to 3.0 mL

12 CLINICAL PHARMACOLOGY

12.1 Mechanism of Action

Somatropin (as well as endogenous GH) binds to a dimeric GH receptor in the cell membrane of target cells resulting in intracellular signal transduction and a host of pharmacodynamic effects. Some of these pharmacodynamic effects are primarily mediated by IGF-I produced in the liver and also locally (e.g., skeletal growth, protein synthesis), while others are primarily a consequence of the direct effects of somatropin (e.g., lipolysis) [see Clinical Pharmacology (12.2)].

12.2 Pharmacodynamics

Tissue Growth

The primary and most intensively studied action of somatropin is the stimulation of linear growth. This effect is demonstrated in children with GHD.

Skeletal Growth

The measurable increase in bone length after administration of somatropin results from its effect on the cartilaginous growth areas of long bones. Studies in vitro have shown that the incorporation of sulfate into proteoglycans is not due to a direct effect of somatropin, but rather is mediated by the somatomedins or insulin-like growth factors (IGFs). The somatomedins, among them IGF-I, are polypeptide hormones which are synthesized in the liver, kidney, and various other tissues. IGF-I levels are low in the serum of hypopituitary dwarfs and hypophysectomized humans or animals, and increase after treatment with somatropin.

Cell Growth

It has been shown that the total number of skeletal muscle cells is markedly decreased in children with short stature lacking endogenous GH compared with normal children, and that treatment with somatropin results in an increase in both the number and size of muscle cells.

Organ Growth

Somatropin influences the size of internal organs, and it also increases red cell mass.

Protein Metabolism

Linear growth is facilitated in part by increased cellular protein synthesis. This synthesis and growth are reflected by nitrogen retention which can be quantitated by observing the decline in urinary nitrogen excretion and blood urea nitrogen following the initiation of somatropin therapy.

Carbohydrate Metabolism

Hypopituitary children sometimes experience fasting hypoglycemia that may be improved by treatment with somatropin. In healthy subjects, large doses of somatropin may impair glucose tolerance. Although the precise mechanism of the diabetogenic effect of somatropin is not known, it is attributed to blocking the action of insulin rather than blocking insulin secretion. Insulin levels in serum actually increase as somatropin levels increase. Administration of human growth hormone to normal adults and patients with growth hormone deficiency results in increases in mean serum fasting and postprandial insulin levels, although mean values remain in the normal range. In addition, mean fasting and postprandial glucose and hemoglobin A1C levels remain in the normal range.

Lipid Metabolism

Somatropin stimulates intracellular lipolysis, and administration of somatropin leads to an increase in plasma free fatty acids and triglycerides. Untreated GHD is associated with increased body fat stores, including increased abdominal visceral and subcutaneous adipose tissue. Treatment of growth hormone deficient patients with somatropin results in a general reduction of fat stores, and decreased serum levels of low density lipoprotein (LDL) cholesterol.

Mineral Metabolism

Administration of somatropin results in an increase in total body potassium and phosphorus and to a lesser extent sodium. This retention is thought to be the result of cell growth. Serum levels of phosphate increase in children with GHD after somatropin therapy due to metabolic activity associated with bone growth. Serum calcium levels are not altered. Although calcium excretion in the urine is increased, there is a simultaneous increase in calcium absorption from the intestine. Negative calcium balance, however, may occasionally occur during somatropin treatment.

Connective Tissue Metabolism

Somatropin stimulates the synthesis of chondroitin sulfate and collagen, and increases the urinary excretion of hydroxyproline.

12.3 Pharmacokinetics

A 180-min IV infusion of Norditropin (33 ng/kg/min) was administered to 9 GHD patients. A mean (±SD) hGH steady state serum level of approximately 23.1 (±15.0) ng/mL was reached at 150 min and a mean clearance rate of approximately 2.3 (±1.8) mL/min/kg or 139 (±105) mL/min for hGH was observed. Following infusion, serum hGH levels had a biexponential decay with a terminal elimination half-life (T1/2) of approximately 21.1 (±5.1) min.

In a study conducted in 18 GHD adult patients, where a SC dose of 0.024 mg/kg or 3 IU/m^2 was given in the thigh, mean (±SD) Cmax values of 13.8 (±5.8) and 17.1 (±10.0) ng/mL were observed for the 4 and 8 mg Norditropin vials, respectively, at approximately 4 to 5 hr. post dose. The mean apparent terminal T1/2 values were estimated to be approximately 7 to 10 hr. However, the absolute bioavailability for Norditropin after the SC route of administration is currently not known.

The aqueous Norditropin cartridge formulation is bioequivalent to the lyophilized Norditropin vial formulation.

13 NONCLINICAL TOXICOLOGY

13.1 Carcinogenesis, Mutagenesis, Impairment of Fertility

Carcinogenicity, mutagenicity, and fertility studies have not been conducted with Norditropin.

14 CLINICAL STUDIES

14.1 Short Stature in Children with Noonan Syndrome

A prospective, open label, randomized, parallel group trial with 21 children was conducted for 2 years to evaluate the efficacy and safety of Norditropin treatment for short stature in children with Noonan syndrome. An additional 6 children were not randomized, but did follow the protocol. After the initial two-year trial, children continued on Norditropin until final height. Retrospective final height and adverse event data were collected from 18 of the 21 subjects who were originally enrolled in the trial and the 6 who had followed the protocol without randomization. Historical reference materials of height velocity and adult height analyses of Noonan patients served as the controls.

The twenty-four (24) (12 female, 12 male) children 3 – 14 years of age received either 0.033 mg/kg/day or 0.066 mg/kg/day of Norditropin subcutaneously which, after the first 2 years, was adjusted based on growth response.

In addition to a diagnosis of Noonan syndrome, key inclusion criteria included bone age determination showing no significant acceleration, prepubertal status, height SDS <-2, and HV SDS <1 during the 12 months pre-treatment. Exclusion criteria were previous or ongoing treatment with growth hormone, anabolic steroids or corticosteroids, congenital heart disease or other serious disease perceived to possibly have major impact on growth, FPG >6.7 mmol/L (>120 mg/dL), or growth hormone deficiency (peak GH levels <10 ng/mL).

Patients obtained a final height (FH) gain from baseline of 1.5 and 1.6 SDS estimated according to the national and the Noonan reference, respectively. A height gain of 1.5 SDS (national) corresponds to a mean height gain of 9.9 cm in boys and 9.1 cm in girls at 18 years of age, while a height gain of 1.6 SDS (Noonan) corresponds to a mean height gain of 11.5 cm in boys and 11.0 cm in girls at 18 years of age.

A comparison of HV between the two treatment groups during the first two years of treatment for the randomized subjects was 10.1 and 7.6 cm/year with 0.066 mg/kg/day versus 8.55 and 6.7 cm/year with 0.033 mg/kg/day, for Year 1 and Year 2, respectively.

Age at start of treatment was a factor for change in height SDS (national reference). The younger the age at start of treatment, the larger the change in height SDS.

Examination of gender subgroups did not identify differences in response to Norditropin.

Not all patients with Noonan syndrome have short stature; some will achieve a normal adult height without treatment. Therefore, prior to initiating Norditropin for a patient with Noonan syndrome, establish that the patient does have short stature.

14.2 Short Stature in Children with Turner Syndrome

Two randomized, parallel group, open label, multicenter studies were conducted in the Netherlands to evaluate the efficacy and safety of Norditropin for the treatment of children with short stature associated with Turner syndrome. Patients were treated to final height in both studies [height velocity (HV) < 2 cm/year]. Changes in height were expressed as standard deviation scores (SDS) utilizing reference data for untreated Turner syndrome patients as well as the national Dutch population.

In Study 1 (the primary study), 68 euthyroid Caucasian patients stratified based on age and baseline height SDS were randomized in a 1:1:1 ratio to three different Norditropin treatment regimens: 0.045 mg/kg/day (Dose A) for the entire study; 0.045 mg/kg/day for the first year and 0.067 mg/kg/day thereafter (Dose B); or 0.045 mg/kg/day for the first year, 0.067 for the second year, and 0.089 mg/kg/day thereafter (Dose C). Overall, at baseline, mean age was 6.5 years, mean height SDS (National standard) was -2.7, and mean HV during the previous year was 6.5 cm/year. Patients also received estrogen therapy after age 12 and following four years of Norditropin treatment if they did not have spontaneous puberty.

Patients were treated for a mean of 8.4 years. As seen in Table 3, overall mean final height was 161 cm in the 46 children who attained final height. Seventy percent of these children reached a final height within the normal range (height SDS > -2 using the National standard). A greater percentage of children in the two escalated dose groups reached normal final height. The mean changes from baseline to final height in height SDS after treatment with Dose B and Dose C were significantly greater than the mean changes observed after treatment with Dose A (utilizing both the National and Turner standards). The mean changes from baseline to final height in height SDS (Turner standard) in Table 3 correspond to mean height gains of 9.4, 14.1 and 14.4 cm after treatment with Doses A, B and C, respectively. The mean changes from baseline to final height in height SDS (National standard) in Table 3 correspond to mean height gains of 4.5, 9.1 and 9.4 cm after treatment with Doses A, B and C, respectively. In each treatment group, peak HV was observed during treatment Year 1, and then gradually decreased each year; during Year 4, HV was less than the pre-treatment HV. However, between Year 2 and Year 6, a greater HV was observed in the two dose escalation groups compared to the 0.045 mg/kg/day group.

Table 3 - Final Height-Related Results After Treatment of Patients with Turner Syndrome with Norditropin in a Randomized, Dose Escalating Study
 | Dose A; 0.045 mg/kg/day; (n=19) | Dose B; up to 0.067 mg/kg/day; (n=15) | Dose C; up to 0.089 mg/kg/day; (n=12) | Total; (n=46)
Baseline height (cm) [Unadjusted (raw) means] | 105 (12) | 108 (12.7) | 107 (11.7) | 106 (11.9)
Final height (cm) | 157 (6.7) | 163 (6.0) | 163 (4.9) | 161 (6.5)
Number (%) of patients reaching normal height (height SDS >-2 using National standard) | 10 (53%) | 12 (80%) | 10 (83%) | 32 (70%)
Height SDS (Turner standard) [Adjusted (least squares) means based on an ANCOVA model including terms for treatment, duration of treatment, age at baseline, bone age at baseline, height SDS at baseline, age at onset of puberty and mid-parental target height SDS]
Final [95% CI] | 1.7 [1.4, 2.0] | 2.5 [2.1, 2.8] [p=0.005 vs. Dose A] | 2.5 [2.1, 2.9] [p=0.006 vs. Dose A] | NA
Change from baseline [95% CI] | 1.5 [1.2, 1.8] | 2.2 [1.9, 2.5] | 2.2 [1.9, 2.6] | NA
Height SDS (National standard)
Final [95% CI] | -1.9 [-2.2, -1.6] | -1.2 [-1.5, -0.9] | -1.2 [-1.6, -0.8] [p=0.008 vs. Dose A] | NA
Change from baseline [95% CI] | 0.7 [0.4, 1.0] | 1.4 [1.1, 1.7] | 1.4 [1.1, 1.8] | NA
Values are expressed as mean (SD) unless otherwise indicated. SDS: Standard deviation score.

In Study 2 (a supportive study), 19 euthyroid Caucasian patients (with bone age ≤13.9 years) were randomized to treatment with 0.067 mg/kg/day of Norditropin as a single subcutaneous dose in the evening, or divided into two doses (1/3 morning and 2/3 evening). All subjects were treated with concomitant ethinyl estradiol. Overall, at baseline, mean age was 13.6 years, mean height SDS (National standard) was -3.5 and mean HV during the previous year was 4.3 cm/year. Patients were treated for a mean of 3.6 years. In that there were no significant differences between the two treatment groups for any linear growth variables, the data from all patients were pooled. Overall mean final height was 155 cm in the 17 children who attained final height. Height SDS changed significantly from -3.5 at baseline to -2.4 at final height (National standard), and from 0.7 to 1.3 at final height (Turner standard).

14.3 Short Stature in Children Born Small for Gestational Age (SGA) with No Catch-up Growth by Age 2-4 Years

A multi-center, randomized, double-blind, two-arm study to final height (Study 1) and a 2-year, multi-center, randomized, double-blind, parallel-group study (Study 2) were conducted to assess the efficacy and safety of Norditropin in children with short stature born SGA with no catch-up growth. Changes in height and height velocity were compared to a national reference population in both studies.

Study 1

The pivotal study included 53 (38 male, 15 female) non-GHD, Dutch children 3-11 years of age with short stature born SGA with no catch-up growth. Catch-up growth was defined as obtaining a height of ≥ 3rd percentile within the first 2 years of life or at a later stage. These prepubertal children needed to meet the following additional inclusion criteria: birth length < 3rd percentile for gestational age, and height velocity (cm/year) for chronological age < 50th percentile. Exclusion criteria included chromosomal abnormalities, signs of a syndrome (except for Silver-Russell syndrome), serious/chronic co-morbid disease, malignancy, and previous rhGH therapy. Norditropin was administered subcutaneously daily at bedtime at a dose of approximately 0.033 (Dose A) or 0.067 mg/kg/day (Dose B) for the entire treatment period. Final height was defined as a height velocity below 2 cm/year. Treatment with Norditropin was continued to final height for up to 13 years. Mean duration of treatment was 9.5 years (boys) and 7.9 years (girls).

38 out of 53 children (72%) reached final height. Sixty-three percent (24 out of 38) of the children who reached final height were within the normal range of their healthy peers (Dutch national reference). For both doses combined, actual mean final height was 171 (SD 6.1) cm in boys and 159 (SD 4.3) cm in girls.

As seen in Table 4, for boys and girls combined, both mean final height SDS (Dose A, -1.8 vs. Dose B, -1.3), and increase in height SDS from baseline to final height (Dose A, 1.4 vs. Dose B, 1.8), were significantly greater after treatment with Dose B (0.067 mg/kg/day). A similar dose response was observed for the increase in height SDS from baseline to Year 2 (Table 4).

Overall mean height velocity at baseline was 5.4 cm/y (SD 1.2; n=29). Height velocity was greatest during the first year of Norditropin treatment and was significantly greater after treatment with Dose B (mean 11.1 cm/y [SD 1.9; n=19]) compared with Dose A (mean 9.7 cm/y [SD 1.3; n=10]).

Table 4 - Study 1: Results for Final Height SDS and Change from Baseline to Final Height in Height SDS Using National Standard After Long-Term Treatment of SGA Children with Norditropin
 | Raw Mean + SD (N)
 | Dose A; 0.033 mg/kg/day | Dose B; 0.067 mg/kg/day | Total
Baseline Height SDS | -3.2 + 0.7 (26) | -3.2 + 0.7 (27) | -3.2 + 0.7 (53)
Adjusted least-squares mean + standard error (N) and [95% confidence intervals]
Height SDS: Change from Baseline at Year 2 | 1.4 + 0.1 (26); [1.1, 1.6] | 1.8 + 0.1 (26); [1.5, 2.0] | Treatment Diff = 0.4; [0.2, 0.7]; p-value = 0.002
Height SDS: Change from Baseline at Final Height [Adjusted (least-squares) means based on an ANCOVA model including terms for treatment, gender, age at baseline, bone age at baseline, height SDS at baseline, duration of treatment, peak GH after stimulation and baseline IGF-1.] | 1.4 + 0.2 (19); [0.9, 1.8] | 1.8 + 0.2 (19); [1.4, 2.2] | Treatment Diff = 0.5; [0.0, 0.9]; p-value = 0.045
Final Height SDS | -1.8 + 0.2 (19); [-2.2, -1.4] | -1.3 + 0.2 (19); [-1.7, -0.9] | Treatment Diff = 0.5; [0.0, 0.9]; p-value = 0.045
Final Height SDS > -2 | 13/19 (68%) | 11/19 (58%) | 24/38 (63%)
SDS: Standard deviation score.

Study 2

In this study, 84 randomized, prepubertal, non-GHD, Japanese children (age 3-8) with short stature born SGA with no catch-up growth were treated for 2 years with 0.033 or 0.067 mg/kg/day of Norditropin subcutaneously daily at bedtime or received no treatment for 1 year. Additional inclusion criteria included birth length or weight SDS ≤ -2 or < 10th percentile for gestational age, height SDS for chronological age ≤ -2, and height velocity SDS for chronological age < 0 within one year prior to Visit 1. Exclusion criteria included diabetes mellitus, history or presence of active malignancy, and serious co-morbid conditions.

As seen in Table 5, for boys and girls combined, there was a dose-dependent increase in height SDS at Year 1 and Year 2. The increase in height SDS from baseline to Year 2 (0.033 mg/kg/day, 0.8 vs. 0.067 mg/kg/day, 1.4) was significantly greater after treatment with 0.067 mg/kg/day. In addition, the increase in height SDS at Year 1 was significantly greater in both active treatment groups compared to the untreated control group.

Table 5 - Study 2: Results for Change from Baseline in Height SDS At Year 1 and Year 2 Using National Standard After Short-Term Treatment of SGA Children with Norditropin
 | Raw Mean + SD (N)
 | No Treatment | 0.033; mg/kg/day | 0.067; mg/kg/day | Total
Height SDS: Baseline | -2.9 + 0.5 (15) | -3.0 + 0.6 (35) | -2.9 + 0.7 (34) | -2.9 + 0.6 (84)
Height SDS: Year 1 | -2.8 + 0.5 (15) | -2.4 + 0.6 (33) | -2.0 + 0.8 (34) | -2.3 + 0.7 (82)
Height SDS: Year 2 | NA | -2.2 + 0.7 (33) | -1.4 + 0.7 (32) | -1.8 + 0.8 (65)
Adjusted least-squares mean + standard error (N) and [95% confidence intervals]
Height SDS: Change from Baseline at Year 1 [Adjusted (least-squares) means based on an ANCOVA model including terms for treatment, gender, age at baseline, and height SDS at baseline. All children remained prepubertal during the study.] | 0.1 + 0.1 (15); [-0.1, 0.2] | 0.6 + 0.1 (33); [0.5, 0.7] | 0.9 + 0.1 (34); [0.8, 1.0]
Height SDS: Change from Baseline at Year 1 [Adjusted (least-squares) means based on an ANCOVA model including terms for treatment, gender, age at baseline, and height SDS at baseline. All children remained prepubertal during the study.] | 0.033 vs. No Treatment: Treatment Diff = 0.5, [0.3, 0.7], p < 0.0001; 0.067 vs. No Treatment: Treatment Diff = 0.8, [0.6, 1.0], p < 0.0001; 0.067 vs. 0.033: Treatment Diff = 0.3, [0.2, 0.5], p-value < 0.0001
Height SDS: Change from Baseline at Year 2 | NA | 0.8 + 0.1 (33); [0.7, 0.9] | 1.4 + 0.1 (32); [1.3, 1.6]
Height SDS: Change from Baseline at Year 2 | 0.067 vs. 0.033: Treatment Diff = 0.6, [0.5, 0.8], p-value < 0.0001
SDS: Standard deviation score.

14.4 Adult Growth Hormone Deficiency (GHD)

A total of six randomized, double-blind, placebo-controlled studies were performed. Two representative studies, one in adult onset (AO) GHD patients and a second in childhood onset (CO) GHD patients, are described below.

Study 1

A single center, randomized, double-blind, placebo-controlled, parallel-group, six month clinical trial was conducted in 31 adults with AO GHD comparing the effects of Norditropin [somatropin (rDNA origin) for injection] and placebo on body composition. Patients in the active treatment arm were treated with Norditropin 0.017 mg/kg/day (not to exceed 1.33 mg/day). The changes from baseline in lean body mass (LBM) and percent total body fat (TBF) were measured by total body potassium (TBP) after 6 months.

Treatment with Norditropin produced a significant (p=0.0028) increase from baseline in LBM compared to placebo (Table 6).

Table 6 - Lean Body Mass (kg) by TBP
 | Norditropin; (n=15) | Placebo; (n=16)
Baseline (mean) | 50.27 | 51.72
Change from baseline at 6 months (mean) | 1.12 | -0.63
Treatment difference (mean) 95% confidence interval p-value | 1.74 (0.65, 2.83) p=0.0028

Analysis of the treatment difference on the change from baseline in percent TBF revealed a significant decrease (p=0.0004) in the Norditropin-treated group compared to the placebo group (Table 7).

Table 7 - Total Body Fat (%) by TBP
 | Norditropin; (n=15) | Placebo; (n=16)
Baseline (mean) | 44.74 | 42.26
Change from baseline at 6 months (mean) | -2.83 | 1.92
Treatment difference (mean) 95% confidence interval p-value | -4.74 (-7.18, -2.30) p=0.0004

Fifteen (48.4%) of the 31 randomized patients were male. The adjusted mean treatment differences on the increase in LBM and decrease in percent TBF from baseline were larger in males compared to females.

Norditropin also significantly increased serum osteocalcin (a marker of osteoblastic activity).

Study 2

A single center, randomized, double-blind, placebo-controlled, parallel-group, dose-finding, six month clinical trial was conducted in 49 men with CO GHD comparing the effects of Norditropin and placebo on body composition. Patients were randomized to placebo or one of three active treatment groups (0.008, 0.016, and 0.024 mg/kg/day). Thirty three percent of the total dose to which each patient was randomized was administered during weeks 1-4, 67% during weeks 5-8, and 100% for the remainder of the study. The changes from baseline in LBM and percent TBF were measured by TBP after 6 months.

Treatment with Norditropin produced a significant (p=0.0079) increase from baseline in LBM compared to placebo (pooled data) (Table 8).

Table 8 - Lean Body Mass (kg) by TBP
 | Norditropin; (n=36) | Placebo; (n=13)
Baseline (mean) | 48.18 | 48.90
Change from baseline at 6 months (mean) | 2.06 | 0.70
Treatment difference (mean) 95% confidence interval p-value | 1.40 (0.39, 2.41) p=0.0079

Analysis of the treatment difference on the change from baseline in percent TBF revealed a significant decrease (p=0.0048) in the Norditropin-treated groups (pooled data) compared to the placebo group (Table 9).

Table 9 - Total Body Fat (%) by TBP
 | Norditropin; (n=36) | Placebo; (n=13)
Baseline (mean) | 34.55 | 34.07
Change from baseline at 6 months (mean) | -6.00 | -1.78
Treatment difference (mean) 95% confidence interval p-value | -4.24 (-7.11, -1.37) p=0.0048

Norditropin also significantly reduced intraabdominal, extraperitoneal and total abdominal fat volume, waist/hip ratio and LDL cholesterol, and significantly increased serum osteocalcin.

Forty four men were enrolled in an open label follow up study and treated with Norditropin for as long as 30 additional months. During this period, the reduction in waist/hip ratio achieved during the initial six months of treatment was maintained.

16 HOW SUPPLIED/STORAGE AND HANDLING

Norditropin NordiFlex prefilled pens [somatropin (rDNA origin) injection] 5 mg/1.5 mL:

Norditropin NordiFlex is individually cartoned in 5 mg/1.5 mL prefilled pens.

- Norditropin NordiFlex 5 mg/1.5 mL (orange) NDC 54868-6146-0

Unused Norditropin NordiFlex pens must be stored at 2-8°C/36-46°F (refrigerator). Do not freeze. Avoid direct light.

5 mg/1.5 mL (orange) prefilled pens:

After the initial injection, a Norditropin NordiFlex (5 mg/1.5 mL) prefilled pen may be EITHER stored in the refrigerator (2-8ºC/36-46ºF) and used within 4 weeks OR stored for up to 3 weeks at not more than 25ºC (77ºF). Discard unused portion.

Table 10 - Storage Options
Norditropin Product Formulation | Before Use | In-use (After 1st injection)
Storage requirement | Storage Option 1; (Refrigeration) | Storage Option 2; (Room temperature)
5 mg | 2-8 ºC/; 36-46 ºF; Until exp date | 2-8 ºC/36-46 ºF; 4 weeks | Up to 25ºC/77ºF; 3 weeks

17 PATIENT COUNSELING INFORMATION

See FDA-approved patient labeling

Patients being treated with Norditropin FlexPro or Norditropin NordiFlex prefilled pens, or Norditropin Cartridges, (and/or their parents) should be informed about the potential risks and benefits associated with somatropin treatment [in particular, see Adverse Reactions (6.1) for a listing of the most serious and/or most frequently observed adverse reactions associated with somatropin treatment in children and adults]. This information is intended to better educate patients (and caregivers); it is not a disclosure of all possible adverse or intended effects.

Patients and caregivers who will administer Norditropin FlexPro or Norditropin NordiFlex prefilled pens, or Norditropin Cartridges, should receive appropriate training and instruction on proper use from the physician or other suitably qualified health care professional. A puncture-resistant container for the disposal of used needles should be strongly recommended. Patients and/or parents should be thoroughly instructed in the importance of proper disposal, and cautioned against any reuse of needles. This information is intended to aid in the safe and effective administration of the medication.

If patients are prescribed Norditropin Cartridges (to be inserted into color-coded NordiPen delivery systems), physicians should instruct patients to read the NordiPen INSTRUCTION booklet provided with the NordiPen delivery systems.

If patients are prescribed Norditropin FlexPro or Norditropin NordiFlex, physicians should instruct patients to read the PATIENT INFORMATION and INSTRUCTIONS FOR USE leaflets provided with the Norditropin FlexPro and Norditropin NordiFlex prefilled pens.

Date of Issue: March 2, 2010

Version: 12

Novo Nordisk® is a registered trademark of Novo Nordisk A/S.

Norditropin®, FlexPro®, NordiPen® and Norditropin NordiFlex® are registered trademarks of Novo Nordisk Health Care AG.

© 2002-2010 Novo Nordisk Health Care AG

For information contact:

Novo Nordisk Inc.

100 College Road West

Princeton, New Jersey 08540, USA

1-888-NOVO-444 (1-888-668-6444)

Manufactured by:

Novo Nordisk A/S

DK-2880 Bagsvaerd, Denmark

Relabeling of "Additional Barcode label" by:

Physicians Total Care, Inc.
Tulsa, OK 74146

PATIENT INFORMATION

Norditropin® (Nor-dee-tro-pin)

(somatropin [rDNA origin]) injection

Read the Patient Information that comes with Norditropin before you start to take it and each time you get a refill. There may be new information. This leaflet does not take the place of talking with your healthcare provider about your medical condition or your treatment.

What is Norditropin?

Norditropin is a prescription medicine given by injection under the skin (subcutaneous) that contains human growth hormone, identical to the growth hormone produced in the human body, used to treat:

- children who are not growing because of low or no growth hormone
- children who are short (in stature) and who have Noonan syndrome or Turner syndrome
- children who are short (in stature) because they were born small (small for gestational age-SGA) and have not caught-up in growth by age 2 to 4 years
- adults who do not make enough growth hormone

Who should not use Norditropin?

Do not use Norditropin if:

- you have a critical illness caused by certain types of heart or stomach surgery, trauma or breathing (respiratory) problems
- you are a child with Prader-Willi syndrome who is severely obese or has breathing problems including sleep apnea
- you have cancer or other tumors
- your healthcare provider tells you that you have certain types of eye problems caused by diabetes
- you are a child with closed bone growth plates (epiphyses)
- you are allergic to any of the ingredients in Norditropin. See the end of this leaflet for a complete list of ingredients in Norditropin.

What should I tell my healthcare provider before I start Norditropin?

Before you take Norditropin, tell your healthcare provider if you:

- have diabetes
- had cancer or any tumor
- have any other medical condition
- are pregnant or plan to become pregnant. It is not known if Norditropin will harm your unborn baby. Talk to your doctor if you are pregnant or plan to become pregnant.
- are breast-feeding or plan to breast-feed. It is not known if Norditropin passes into your breast milk. You and your healthcare provider should decide if you will take Norditropin while you breast-feed.

Tell your healthcare provider about all the medicines you take, including prescription and non-prescription medicines, vitamins, and herbal supplements. Norditropin may affect how other medicines work, and other medicines may affect how Norditropin works.

Especially tell your healthcare provider if you take:

- glucocorticoid medication
- thyroid hormone
- insulin or other medicine for diabetes
- medicines that are metabolized by the liver
- estrogen replacement medicines

Ask your healthcare provider if you are not sure if any of your medicines are the kind listed above. Keep a list of your medicines with you and show it to your healthcare provider and pharmacist when you get a new medicine.

How should I use Norditropin?

- Read the detailed Instructions for Use that come with Norditropin. Your healthcare provider will show you how to inject Norditropin.
- Take Norditropin exactly as prescribed.
- Norditropin FlexPro pens, NordiFlex pens and cartridges are for use by one person only.
- Novo Nordisk disposable needles are designed to be used with Norditropin for each injection.
- Always keep the pen cap closed on Norditropin when you are not using it.
- Norditropin comes in 3 dose strengths for FlexPro prefilled color coded pens, 4 dose strengths for NordiFlex prefilled color coded pens, and 2 dose strengths for color coded cartridges.
- If you inject too much Norditropin, call your healthcare provider.
- If you miss a dose, take it as soon as you remember. If it is almost time for your next dose, skip the missed dose. Just take the next dose at your regular time. Do not take 2 doses at the same time unless your healthcare provider tells you to. If you are not sure about your dosing, call your healthcare provider.
- Throw away Norditropin when the cartridge is empty.
- Refer to the Instructions for Use about what to do if you have less than a full dose left in your pen.

What are the possible side effects of Norditropin?

Norditropin can cause serious side effects, including:

- high risk of death in people who have critical illnesses because of heart or stomach surgery, trauma or serious breathing (respiratory) problems
- high risk of death in children with Prader-Willi syndrome who are severely obese or have breathing problems, including sleep apnea
- return of tumor or cancerous growths
- high blood sugar (hyperglycemia)
- increase in pressure in the skull (intracranial hypertension). If you have headaches, eye problems, nausea or vomiting, contact your healthcare provider right away.
- swollen hands and feet due to fluid retention
- decrease in thyroid hormone levels. Your healthcare provider will do blood tests to check your thyroid hormone levels.
- hip and knee pain or a limp in children (slipped capital femoral epiphysis)
- worsening of curvature of the spine (scoliosis)
- middle ear infection, hearing problems or ear problems in patients with Turner syndrome
- redness, itching and tissue weakness in the area you inject
- increase in phosphorus, alkaline phosphatase and parathyroid hormone levels in your blood. Your healthcare provider will do blood tests to check this.

The most common side effects of Norditropin include:

- headaches
- muscle pain
- joint stiffness
- high blood sugar (hyperglycemia)
- sugar in your urine (glucosuria)
- swollen hands and feet due to fluid retention
- redness and itching in the area you inject

Talk to your healthcare provider if you have any side effect that bothers you or that does not go away.

These are not all the possible side effects of Norditropin. For more information, ask your healthcare provider or pharmacist.

Call your healthcare provider for medical advice about side effects. You may report side effects to FDA at 1-800-FDA-1088 (1-800-332-1088). You may also report side effects to Novo Nordisk at 1-888-NOVO-444 (1-888-668-6444).

How do I store Norditropin?

Unused Norditropin FlexPro and NordiFlex pens, and cartridges:

- Keep in a refrigerator between 36ºF to 46ºF (2ºC to 8ºC).
- Do not freeze or expose Norditropin to heat.
- Keep Norditropin away from direct light.
- Do not use Norditropin that has been frozen or in temperatures warmer than 77ºF (25ºC).
- Do not use Norditropin after the expiration date printed on the carton and the pen or cartridge.

After the first injection

- Norditropin FlexPro, NordiFlex and cartridge 5 mg/1.5 mL (orange):
  - either store in the refrigerator between 36ºF to 46ºF (2ºC to 8ºC) and use within 4 weeks
  - orkeep for up to 3 weeks at no warmer than 77ºF(25ºC).
  - Throw away any unused medicine.
- Norditropin FlexPro and NordiFlex 10 mg/1.5mL (blue):
  - either store in the refrigerator between 36ºF to 46ºF (2ºC to 8º C) and use within 4 weeks.
  - or keep for up to 3 weeks at no warmer than 77 ºF (25ºC).
  - Throw away any unused medicine.
- Norditropin FlexPro, NordiFlex and cartridge 15 mg/1.5 mL (green):
  - store in the refrigerator between 36ºF to 46ºF (2ºC to 8ºC) and use within 4 weeks
  - Throw away any unused medicine after 4 weeks.
- Norditropin NordiFlex pens 30 mg/3 mL (purple):
  - store in the refrigerator between 36ºF to 46ºF (2ºC to 8ºC) and use within 4 weeks
  - Throw away any unused medicine after 4 weeks

General Information about Norditropin.

Medicines are sometimes prescribed for purposes other than those listed in Patient Information. Do not use Norditropin for a condition for which it was not prescribed. Do not give Norditropin to other people, even if they have the same symptoms that you have. It may harm them.

This Patient Information summarizes the most important information about Norditropin. If you would like more information, talk with your healthcare provider. You can ask your pharmacist or healthcare provider for information about Norditropin that is written for healthcare professionals.

What are the ingredients in Norditropin?

Active ingredient: somatropin (rDNA origin)

Inactive ingredients: Histidine, Poloxamer 188, Phenol, Mannitol, HCl/NaOH (as needed) and Water for Injection

Date of Issue: March 2, 2010

Version: 7

For assistance or further information, write to:

Novo Nordisk Inc.

100 College Road West

Princeton, NJ 08540, USA

1-888-NOVO-444 (1-888-668-6444)

norditropin-us.com

US Patent Nos. 6,235,004; 6,004,297; 6,582,404; 6,716,198; 6,899,699; 5,849,704; 5,691,169; 5,618,697 and other patents pending.

Norditropin®, FlexPro®, Norditropin NordiFlex® and NordiFlex PenMate® are registered trademarks of Novo Nordisk Health Care AG.

Novo Nordisk® is a registered trademark of Novo Nordisk A/S.

© 2004-2010 Novo Nordisk Health Care AG

Manufactured by:

Novo Nordisk A/S

DK-2880 Bagsvaerd, Denmark

INSTRUCTIONS FOR USE

Norditropin NordiFlex®

Somatropin (rDNA origin) injection

5 mg/1.5 mL Prefilled Pen

Using the disposable Norditropin NordiFlex® 5 mg/1.5 mL Prefilled Pen

Norditropin NordiFlex 5 mg/1.5 mL is a multi-dose, disposable, prefilled pen with liquid growth hormone able to deliver doses from 0.025 to 1.5 mg. The dose can be adjusted in increments of 0.025 mg. Your doctor will determine the correct dose for you. Norditropin NordiFlex prefilled pen is designed to be used with NovoFine® disposable needles (sold separately). Norditropin NordiFlex prefilled pen is not recommended for people who are blind or have trouble seeing unless they have the help of a sighted individual trained to use Norditropin NordiFlex.

Please read these instructions carefully before using this pen

1 Preparing Norditropin NordiFlex 5 mg/1.5 mL for injection

A. Pull off the pen cap and check if the growth hormone solution is clear and colorless by turning Norditropin NordiFlex upside down once or twice and view the solution through the residual scale window. DO NOT use Norditropin NordiFlex if the growth hormone solution is cloudy or contains particles. Use it only if it is clear and colorless.

Wash hands well and dry completely.

Wipe the front rubber stopper on the threaded plastic cap with an alcohol swab.

B. Place a new NovoFine disposable needle onto Norditropin NordiFlex immediately before use. Remove the protective tab from the disposable needle and screw the needle tightly onto Norditropin NordiFlex. Pull off the outer and inner needle caps. Never place a disposable needle on your Norditropin NordiFlex until you are ready to give an injection. Remove the needle immediately after use. If the needle is not removed, some growth hormone may be expelled from Norditropin NordiFlex.

2 Performing an air shot

Do an air shot before starting a new Norditropin NordiFlex as follows:

Small amounts of air may collect in the needle and cartridge. To avoid injecting air and ensure proper dosing, set the dosage selector to 0.025 mg. Each line between labeled dosages is 0.025 mg.

C. Dial 0.025 mg

D. Hold Norditropin NordiFlex with the needle pointing up, tap the cartridge gently with your finger a few times to raise any air bubbles to the top of the cartridge.

E. Still holding Norditropin NordiFlex with the needle up, press the push button all the way in. A drop of growth hormone should appear at the needle tip. If not, repeat the procedure, no more than 4 times.

If a drop of growth hormone still does not appear, call 1-888-NOVO-444 for help.

3 Setting the dose

F. Check that the dose selector is set at 0.0. Dial the number of mg (milligram) that you need to inject. The dose can be changed up or down by turning the dose selector in either direction. When dialing back, be careful not to press the push button as growth hormone liquid will come out.

DO NOT use the clicking sound as a guide for selecting dose.

The numbers on the residual scale can be used to estimate the mg left in the cartridge. DO NOT use these numbers to measure the growth hormone dose.

You cannot set a dose higher than the number of mg left in the cartridge. Use a new Norditropin NordiFlex pen to inject the remaining amount of your dose. Be sure to remember the dose already received with the first dose. For example, if your dose is 0.6 mg and you can only set the dose selector to 0.4 mg, you will need to inject an additional 0.2 mg with a new Norditropin NordiFlex pen.

4 Giving the injection

Use the injection procedure recommended by your doctor or healthcare professional.

G. This product is for subcutaneous use only. Insert the needle under the skin and deliver the dose by pressing the push button all the way in. Press the push button only when injecting.

After the injection, the needle should remain under the skin for at least 6 seconds. Keep the push button fully depressed until the needle is removed from the skin. This will ensure that the full dose has been delivered. Vary the injection site using the injection procedure recommended by your doctor.

After the injection, check the dosage indicator window to make sure it shows zero (0.0).

If zero does not appear, you did not receive the full dose. Call 1-888-NOVO-444 for assistance.

5 Removing the needle

H. After the injection, remove the needle without recapping and dispose of it in a puncture-resistant container. Used needles should be placed in sharps container (such as red biohazard containers), hard plastic containers (such as detergent bottles), or metal containers (such as an empty coffee can). Such containers should be sealed and disposed of properly.

It is important that you use a new needle for each injection. Healthcare professionals, relatives and other caregivers should follow general precautionary measures for removal and disposal of needles to eliminate the risk of unintended needle stick injuries.

When the cartridge is empty, throw away Norditropin NordiFlex without the needle attached.

6 Maintenance

Norditropin NordiFlex should be handled with care. Protect Norditropin NordiFlex from dust, dirt, and direct sunlight.

You can clean the outside of Norditropin NordiFlex by wiping it with a soft cloth moistened with water. Do not soak Norditropin NordiFlex in alcohol, wash, or lubricate it.

7 Important Notes

- Store unused Norditropin NordiFlex pens in a refrigerator (2ºC-8ºC/36ºF-46ºF). After the initial injection, Norditropin NordiFlex 5 mg/1.5 mL may be EITHER stored in the refrigerator (2-8ºC/36-46ºF) and used within 4 weeks OR may be stored for up to 3 weeks at not more than 25ºC (77ºF).
- Remember to perform an air shot before starting a new Norditropin NordiFlex or before the injection if you dropped or knocked the pen against a hard surface. See diagrams C, D and E.
- If you need to perform more than 4 air shots before the first use of Norditropin NordiFlex to get a droplet of growth hormone at the needle tip, DO NOT use Norditropin NordiFlex. Call 1-888-NOVO-444 for help.
- Take care not to drop Norditropin NordiFlex or knock it against a hard surface.
- DO NOT leave Norditropin NordiFlex in a car or other location where it can get too hot or too cold.
- Always have a spare Norditropin NordiFlex disposable pen in order to avoid running out of this product.
- Norditropin NordiFlex is designed to be used with NovoFine disposable needles.
- NEVER place a needle on Norditropin NordiFlex until you are ready to use it. Remove the needle right after use without recapping.
- Throw away used needles properly, so people will not be harmed.
- Throw away the used Norditropin NordiFlex, without the needle attached.
- To avoid spread of disease, do not let anyone else use your Norditropin NordiFlex, even if you attach a new needle.
- Keep Norditropin NordiFlex out of the reach of children.
- Novo Nordisk is not responsible for harm due to using Norditropin NordiFlex with products that are not recommended by Novo Nordisk.

8 Warranty

If your Norditropin NordiFlex is defective in materials or workmanship, Novo Nordisk Inc. will replace it at no charge if you mail the defective unit, postage prepaid to:

Novo Nordisk Inc.

Product Safety

100 College Road West

Princeton, NJ 08540, USA

INSTRUCTIONS FOR USE

Norditropin NordiFlex®

Somatropin (rDNA origin) injection

10 mg/1.5 mL Prefilled Pen

Using the disposable Norditropin NordiFlex® 10 mg/1.5 mL Prefilled Pen

Norditropin NordiFlex 10 mg/1.5 mL is a multi-dose, disposable, prefilled pen with liquid growth hormone able to deliver doses from 0.05 to 3.0 mg. The dose can be adjusted in increments of 0.05 mg. Your doctor will determine the correct dose for you. Norditropin NordiFlex prefilled pen is designed to be used with NovoFine® disposable needles (sold separately). Norditropin NordiFlex prefilled pen is not recommended for people who are blind or have trouble seeing unless they have the help of a sighted individual trained to use Norditropin NordiFlex.

Please read these instructions carefully before using this pen

1 Preparing Norditropin NordiFlex 10 mg/1.5 mL for injection

A. Pull off the pen cap and check if the growth hormone solution is clear and colorless by turning Norditropin NordiFlex upside down once or twice and view the solution through the residual scale window. DO NOT use Norditropin NordiFlex if the growth hormone solution is cloudy or contains particles. Use it only if it is clear and colorless.

Wash hands well and dry completely.

Wipe the front rubber stopper on the threaded plastic cap with an alcohol swab.

B. Place a new NovoFine disposable needle onto Norditropin NordiFlex immediately before use. Remove the protective tab from the disposable needle and screw the needle tightly onto Norditropin NordiFlex. Pull off the outer and inner needle caps. Never place a disposable needle on your Norditropin NordiFlex until you are ready to give an injection. Remove the needle immediately after use. If the needle is not removed, some growth hormone may be expelled from Norditropin NordiFlex.

2 Performing an air shot

Do an air shot before starting a new Norditropin NordiFlex as follows:

Small amounts of air may collect in the needle and cartridge. To avoid injecting air and ensure proper dosing, set the dosage selector to 0.05 mg. Each line between labeled dosages is 0.05 mg.

C. Dial 0.05 mg

D. Hold Norditropin NordiFlex with the needle pointing up, tap the cartridge gently with your finger a few times to raise any air bubbles to the top of the cartridge.

E. Still holding Norditropin NordiFlex with the needle up, press the push button all the way in. A drop of growth hormone should appear at the needle tip. If not, repeat the procedure, no more than 4 times.

If a drop of growth hormone still does not appear, call 1-888-NOVO-444 for help.

3 Setting the dose

F. Check that the dose selector is set at 0.0. Dial the number of mg (milligram) that you need to inject. The dose can be changed up or down by turning the dose selector in either direction. When dialing back, be careful not to press the push button as growth hormone liquid will come out.

DO NOT use the clicking sound as a guide for selecting dose.

The numbers on the residual scale can be used to estimate the mg left in the cartridge. DO NOT use these numbers to measure the growth hormone dose.

You cannot set a dose higher than the number of mg left in the cartridge. Use a new Norditropin NordiFlex pen to inject the remaining amount of your dose. Be sure to remember the dose already received with the first dose. For example, if your dose is 0.6 mg and you can only set the dose selector to 0.4 mg, you will need to inject an additional 0.2 mg with a new Norditropin NordiFlex pen.

4 Giving the injection

Use the injection procedure recommended by your doctor or healthcare professional.

G. This product is for subcutaneous use only. Insert the needle under the skin and deliver the dose by pressing the push button all the way in. Press the push button only when injecting.

After the injection, the needle should remain under the skin for at least 6 seconds. Keep the push button fully depressed until the needle is removed from the skin. This will ensure that the full dose has been delivered. Vary the injection site using the injection procedure recommended by your doctor.

After the injection, check the dosage indicator window to make sure it shows zero (0.0).

If zero does not appear, you did not receive the full dose. Call 1-888-NOVO-444 for assistance.

5 Removing the needle

H. After the injection, remove the needle without recapping and dispose of it in a puncture-resistant container. Used needles should be placed in sharps container (such as red biohazard containers), hard plastic containers (such as detergent bottles), or metal containers (such as an empty coffee can). Such containers should be sealed and disposed of properly.

It is important that you use a new needle for each injection. Healthcare professionals, relatives and other caregivers should follow general precautionary measures for removal and disposal of needles to eliminate the risk of unintended needle stick injuries.

When the cartridge is empty, throw away Norditropin NordiFlex without the needle attached.

6 Maintenance

Norditropin NordiFlex should be handled with care. Protect Norditropin NordiFlex from dust, dirt, and direct sunlight.

You can clean the outside of Norditropin NordiFlex by wiping it with a soft cloth moistened with water. Do not soak Norditropin NordiFlex in alcohol, wash, or lubricate it.

7 Important Notes

- Store unused Norditropin NordiFlex pens in a refrigerator (2ºC-8ºC/36ºF-46ºF). After the initial injection, Norditropin NordiFlex 10 mg/1.5 mL may be EITHER stored in the refrigerator (2-8ºC/36-46ºF) and used within 4 weeks OR may be stored for up to 3 weeks at not more than 25ºC (77ºF).
- Remember to perform an air shot before starting a new Norditropin NordiFlex or before the injection if you dropped or knocked the pen against a hard surface. See diagrams C, D and E.
- If you need to perform more than 4 air shots before the first use of Norditropin NordiFlex to get a droplet of growth hormone at the needle tip, DO NOT use Norditropin NordiFlex. Call 1-888-NOVO-444 for help.
- Take care not to drop Norditropin NordiFlex or knock it against a hard surface.
- DO NOT leave Norditropin NordiFlex in a car or other location where it can get too hot or too cold.
- Always have a spare Norditropin NordiFlex disposable pen in order to avoid running out of this product.
- Norditropin NordiFlex is designed to be used with NovoFine disposable needles.
- NEVER place a needle on Norditropin NordiFlex until you are ready to use it. Remove the needle right after use without recapping.
- Throw away used needles properly, so people will not be harmed.
- Throw away the used Norditropin NordiFlex, without the needle attached.
- To avoid spread of disease, do not let anyone else use your Norditropin NordiFlex, even if you attach a new needle.
- Keep Norditropin NordiFlex out of the reach of children.
- Novo Nordisk is not responsible for harm due to using Norditropin NordiFlex with products that are not recommended by Novo Nordisk.

8 Warranty

If your Norditropin NordiFlex is defective in materials or workmanship, Novo Nordisk Inc. will replace it at no charge if you mail the defective unit, postage prepaid to:

Novo Nordisk Inc.

Product Safety

100 College Road West

Princeton, NJ 08540, USA

INSTRUCTIONS FOR USE

Norditropin NordiFlex®

Somatropin (rDNA origin) injection

15 mg/1.5 mL Prefilled Pen

Using the disposable Norditropin NordiFlex® 15 mg/1.5 mL Prefilled Pen

Norditropin NordiFlex 15 mg/1.5 mL is a multi-dose, disposable, prefilled pen with liquid growth hormone able to deliver doses from 0.075 to 4.5 mg. The dose can be adjusted in increments of 0.075 mg. Your doctor will determine the correct dose for you. Norditropin NordiFlex prefilled pen is designed to be used with NovoFine® disposable needles (sold separately). Norditropin NordiFlex prefilled pen is not recommended for people who are blind or have trouble seeing unless they have the help of a sighted individual trained to use Norditropin NordiFlex.

Please read these instructions carefully before using this pen

1 Preparing Norditropin NordiFlex 15 mg/1.5 mL for injection

A. Pull off the pen cap and check if the growth hormone solution is clear and colorless by turning Norditropin NordiFlex upside down once or twice and view the solution through the residual scale window. DO NOT use Norditropin NordiFlex if the growth hormone solution is cloudy or contains particles. Use it only if it is clear and colorless.

Wash hands well and dry completely.

Wipe the front rubber stopper on the threaded plastic cap with an alcohol swab.

B. Place a new NovoFine disposable needle onto Norditropin NordiFlex immediately before use. Remove the protective tab from the disposable needle and screw the needle tightly onto Norditropin NordiFlex. Pull off the outer and inner needle caps. Never place a disposable needle on your Norditropin NordiFlex until you are ready to give an injection. Remove the needle immediately after use. If the needle is not removed, some growth hormone may be expelled from Norditropin NordiFlex.

2 Performing an air shot

Do an air shot before starting a new Norditropin NordiFlex as follows:

Small amounts of air may collect in the needle and cartridge. To avoid injecting air and ensure proper dosing, set the dosage selector to 0.075 mg. Each line between labeled dosages is 0.075 mg.

C. Dial 0.075 mg

D. Hold Norditropin NordiFlex with the needle pointing up, tap the cartridge gently with your finger a few times to raise any air bubbles to the top of the cartridge.

E. Still holding Norditropin NordiFlex with the needle up, press the push button all the way in. A drop of growth hormone should appear at the needle tip. If not, repeat the procedure, no more than 4 times.

If a drop of growth hormone still does not appear, call 1-888-NOVO-444 for help.

3 Setting the dose

F. Check that the dose selector is set at 0.0. Dial the number of mg (milligram) that you need to inject. The dose can be changed up or down by turning the dose selector in either direction. When dialing back, be careful not to press the push button as growth hormone liquid will come out.

DO NOT use the clicking sound as a guide for selecting dose.

The numbers on the residual scale can be used to estimate the mg left in the cartridge. DO NOT use these numbers to measure the growth hormone dose.

You cannot set a dose higher than the number of mg left in the cartridge. Use a new Norditropin NordiFlex pen to inject the remaining amount of your dose. Be sure to remember the dose already received with the first dose. For example, if your dose is 0.6 mg and you can only set the dose selector to 0.3 mg, you will need to inject an additional 0.3 mg with a new Norditropin NordiFlex pen.

4 Giving the injection

Use the injection procedure recommended by your doctor or healthcare professional.

G. This product is for subcutaneous use only. Insert the needle under the skin and deliver the dose by pressing the push button all the way in. Press the push button only when injecting.

After the injection, the needle should remain under the skin for at least 6 seconds. Keep the push button fully depressed until the needle is removed from the skin. This will ensure that the full dose has been delivered. Vary the injection site using the injection procedure recommended by your doctor.

After the injection, check the dosage indicator window to make sure it shows zero (0.0).

If zero does not appear, you did not receive the full dose. Call 1-888-NOVO-444 for assistance.

5 Removing the needle

H. After the injection, remove the needle without recapping and dispose of it in a puncture-resistant container. Used needles should be placed in sharps container (such as red biohazard containers), hard plastic containers (such as detergent bottles), or metal containers (such as an empty coffee can). Such containers should be sealed and disposed of properly.

It is important that you use a new needle for each injection. Healthcare professionals, relatives and other caregivers should follow general precautionary measures for removal and disposal of needles to eliminate the risk of unintended needle stick injuries.

When the cartridge is empty, throw away Norditropin NordiFlex without the needle attached.

6 Maintenance

Norditropin NordiFlex should be handled with care. Protect Norditropin NordiFlex from dust, dirt, and direct sunlight.

You can clean the outside of Norditropin NordiFlex by wiping it with a soft cloth moistened with water. Do not soak Norditropin NordiFlex in alcohol, wash, or lubricate it.

7 Important Notes

- Store unused Norditropin NordiFlex pens in a refrigerator (2ºC-8ºC/36ºF-46ºF). After the initial injection, keep Norditropin NordiFlex 15 mg/1.5 mL refrigerated and use within 4 weeks.
- Remember to perform an air shot before starting a new Norditropin NordiFlex or before the injection if you dropped or knocked the pen against a hard surface. See diagrams C, D and E.
- If you need to perform more than 4 air shots before the first use of Norditropin NordiFlex to get a droplet of growth hormone at the needle tip, DO NOT use Norditropin NordiFlex. Call 1-888-NOVO-444 for help.
- Take care not to drop Norditropin NordiFlex or knock it against a hard surface.
- DO NOT leave Norditropin NordiFlex in a car or other location where it can get too hot or too cold.
- Always have a spare Norditropin NordiFlex disposable pen in order to avoid running out of this product.
- Norditropin NordiFlex is designed to be used with NovoFine disposable needles.
- NEVER place a needle on Norditropin NordiFlex until you are ready to use it. Remove the needle right after use without recapping.
- Throw away used needles properly, so people will not be harmed.
- Throw away the used Norditropin NordiFlex, without the needle attached.
- To avoid spread of disease, do not let anyone else use your Norditropin NordiFlex, even if you attach a new needle.
- Keep Norditropin NordiFlex out of the reach of children.
- Novo Nordisk is not responsible for harm due to using Norditropin NordiFlex with products that are not recommended by Novo Nordisk.

8 Warranty

If your Norditropin NordiFlex is defective in materials or workmanship, Novo Nordisk Inc. will replace it at no charge if you mail the defective unit, postage prepaid to:

Novo Nordisk Inc.

Product Safety

100 College Road West

Princeton, NJ 08540, USA

INSTRUCTIONS FOR USE

Norditropin NordiFlex®

Somatropin (rDNA origin) injection

30 mg/3 mL Prefilled Pen

Using the disposable Norditropin NordiFlex® 30 mg/3 mL Prefilled Pen

Norditropin NordiFlex 30 mg/3 mL is a multi-dose, disposable, prefilled pen with liquid growth hormone able to deliver doses from 0.1 to 6.0 mg. The dose can be adjusted in increments of 0.1 mg. Your doctor will determine the correct dose for you. Norditropin NordiFlex prefilled pen is designed to be used with NovoFine® disposable needles (sold separately). Norditropin NordiFlex prefilled pen is not recommended for people who are blind or have trouble seeing unless they have the help of a sighted individual trained to use Norditropin NordiFlex.

Please read these instructions carefully before using this pen

1 Preparing Norditropin NordiFlex 30 mg/3 mL for Injection

A. Pull off the pen cap and check if the growth hormone solution is clear and colorless by turning the Norditropin NordiFlex upside down once or twice and view the solution through the residual scale window. DO NOT use Norditropin NordiFlex if the growth hormone solution is cloudy or contains particles. Use it only if it is clear and colorless.

Wash hands well and dry completely.

Wipe the front rubber stopper on the needle thread with an alcohol swab.

B. Place a new NovoFine disposable needle onto Norditropin NordiFlex immediately before use. Remove the protective tab from the disposable needle and screw the needle tightly onto Norditropin NordiFlex. Pull off the outer and inner needle caps. Never place a disposable needle on your Norditropin NordiFlex until you are ready to give an injection. Remove the needle immediately after use. If the needle is not removed, some liquid may be expelled from Norditropin NordiFlex.

2 Performing an Air Shot

Do an air shot before starting a new Norditropin NordiFlex as follows:

Small amounts of air may collect in the needle and cartridge. To ensure proper dosing and to avoid injecting air, you must perform an air shot before administering your first injection.

C. Dial the dosage selector to 0.1 mg. Each line between labeled dosages is 0.1 mg.

D. Hold Norditropin NordiFlex with the needle pointing up, tap the cartridge gently with your finger a few times to make any air bubbles rise to the top of the cartridge.

E. Still holding Norditropin NordiFlex with the needle up, press the push button all the way in. A drop of liquid should appear at the needle tip. If not, repeat the above steps, no more than 4 times.

If a drop of liquid still does not appear, call 1-888-NOVO-444 for help.

3 Setting the Dose

F. Check that the dose selector is set at 0.0. Dial the number of mg (milligram) that you need to inject. If you dial more than your dose, the dose can be changed up or down by turning the dose selector in either direction. When dialing back, be careful not to press the push button as liquid will come out.

Use dosage indicator, NOT the clicking sound, as a guide for selecting the dose.

The numbers on the residual scale can be used to estimate the mg left in the cartridge. DO NOT use these numbers to measure the dose.

You cannot set a dose higher than the number of mg left in the cartridge. Use a new Norditropin NordiFlex pen to inject the remaining amount of your dose. Be sure to remember the dose already received with the first dose. For example, if your dose is 0.6 mg and you can only set the dose selector to 0.3 mg. You will need to inject an additional 0.3 mg with a new Norditropin NordiFlex pen.

4 Giving the Injection

Use the injection technique recommended by your healthcare professional.

G. This product is for subcutaneous use only. Insert the needle under the skin and press the push button as far as it goes to deliver the dose. To ensure that the full dose is injected keep the needle in the skin for at least 6 seconds after injection with your thumb on the push button. Keep the push button fully pushed in until after the needle has been removed from the skin.

After the injection, check the dosage indicator window to make sure it shows zero (0.0).

If zero does not appear, you did not receive the full dose. Call 1-888-NOVO-444 for assistance.

Note:

Always press the push button to inject the dose. Turning the dosage selector will not inject the dose.

5 Removing the NovoFine Disposable Needle

H. After the injection, remove the needle without recapping and dispose of it in a puncture-resistant container. Used needles should be placed in sharps container (such as red biohazard containers), hard plastic containers (such as detergent bottles), or metal containers (such as an empty coffee can). Such containers should be sealed and disposed of properly.

It is important that you use a new needle for each injection. Healthcare professionals, relatives and other caregivers should follow general precautionary measures for removal and disposal of needles to reduce the risk of unintended needle stick injuries.

When the cartridge is empty, dispose of Norditropin NordiFlex without the needle attached.

6 Maintenance

Handle Norditropin NordiFlex with care. Protect Norditropin NordiFlex from dust, dirt, and direct sunlight.

You can clean the outside of Norditropin NordiFlex by wiping it with a soft cloth moistened with water. Do not soak Norditropin NordiFlex in alcohol, wash, or lubricate it.

7 Important Things to Know

- Norditropin NordiFlex 30 mg/3 mL cannot be used with the NordiFlex PenMate® auto-insertion accessory.
- Store unused Norditropin NordiFlex pens in a refrigerator (2ºC - 8ºC/36ºF - 46ºF). After the initial injection, keep Norditropin NordiFlex 30 mg/3 mL refrigerated and use within 4 weeks.
- Remember to perform an air shot before starting a new Norditropin NordiFlex or before the injection if you dropped or knocked the pen against a hard surface. See diagrams C, D and E.
- If you need to perform more than 4 air shots before the first use of Norditropin NordiFlex to get a droplet of liquid at the needle tip, DO NOT use Norditropin NordiFlex. Call 1-888-NOVO-444 for help.
- Take care not to drop Norditropin NordiFlex or knock it against a hard surface.
- DO NOT leave Norditropin NordiFlex in a car or other location where it can get too hot or too cold.
- Always have a spare Norditropin NordiFlex disposable pen in order to avoid running out of this product.
- Norditropin NordiFlex is designed to be used with NovoFine disposable needles.
- NEVER place a needle on Norditropin NordiFlex until you are ready to use it. Remove the needle right after use without recapping.
- Dispose of used needles properly, so people will not be harmed.
- Dispose of used Norditropin NordiFlex, without the needle attached.
- To avoid spread of disease, do not let anyone else use your Norditropin NordiFlex, even if you attach a new needle.
- Keep the Norditropin NordiFlex out of the reach of children.
- Novo Nordisk is not responsible for harm due to using the Norditropin NordiFlex with products that are not recommended by Novo Nordisk.

8 Customer Satisfaction

Customer service and satisfaction are our top concerns. If you have any questions about Norditropin NordiFlex prefilled pens please call Novo Nordisk Inc. at 1-888-NOVO-444.

INSTRUCTIONS FOR USE

Norditropin® FlexPro®

(somatropin [rDNA origin] injection)

5 mg/1.5 mL (orange) Prefilled Pen

Read these instructions before using your Norditropin® FlexPro® pen.

Norditropin FlexPro contains 5 mg human growth hormone solution and delivers doses from 0.025 mg to 2 mg, in increments of 0.025 mg. Norditropin FlexPro is made to be used with Novo Nordisk® disposable needles. Needles are not included with Norditropin FlexPro.

Prepare your Norditropin FlexPro pen

A.

- Pull off the pen cap.
- Check that the liquid in the pen is clear and colorless by tipping it upside down 1 or 2 times. If the liquid looks unclear or cloudy, do not use the pen.
- Wash hands well and dry them.
- Wipe the front stopper on the needle thread with an alcohol swab.

B.

- Take a new disposable needle.
- Tear the paper tab off and screw the needle straight onto the pen.
- Make sure the needle is on tight.
- Never place a disposable needle on your Norditropin FlexPro pen until you are ready to give an injection.

C.

- Pull off the outer needle cap and inner needle cap and throw them both away.
- If you try to put the needle caps back on, you may accidentally hurt yourself with the needle.
- A drop of liquid may appear at the needle tip. This is normal.

Important:

- Always use a new needle for each injection. This will help prevent contamination.
- Never bend or damage the needle.

Check the growth hormone flow (airshot)

Make sure that you receive your full dose by checking the growth hormone flow (performing an airshot) before you select and inject your first dose from a new pen.

D. Turn the dose selector to select 0.025 mg. This is the smallest amount of medicine for a dose.

E.

- Hold the pen with the needle pointing up.
- Tap the top of the pen gently a few times to let any air bubbles rise to the top.

F.

- Press the dose button until the "0" in the display window lines up with the pointer and a drop of liquid appears at the needle tip.
- If no drop appears, repeat steps D, E and F up to 6 times.
- If no drop appears after these attempts, change the needle and repeat steps D, E and F one more time.
- If a drop of liquid still does not appear, call (1-888-668-6444) for help.

Important:

- Be careful not to drop Norditropin FlexPro pen or knock it against a hard surface. If this happens you will need to repeat the airshot.
- Always make sure that a drop appears at the needle tip after completing your airshot.

Select your dose

Use the dose selector on your Norditropin FlexPro pen to make sure you have the exact dose selected. You can select up to 2 mg per dose.

G.

- Select or adjust the dose you need by turning the dose selector forwards or backwards until the right number of mg lines up with the pointer.
- When dialing back, be careful not to press the dose button as liquid will come out.
- To guide you, the dose selector clicks differently when turned forwards, backwards or past the number of mg that is left in the pen.
- When the pen has less than 2 mg, the dose selector stops at the number of mg that is left in the pen.

How much growth hormone is left in the pen?

You can use the growth hormone scale to see how much growth hormone is left in the pen.

You can use the dose selector to see exactly how much growth hormone is left in the pen. If the pen contains less than 2 mg, turn the dose selector until it stops. The figure that lines up with the pointer shows how many mg is left in the pen.

- You cannot set a dose higher than the number of mg left in the pen.
- If there is not enough Norditropin left in the pen to deliver your full dose, use a new Norditropin FlexPro pen to inject the remaining amount of your dose or contact your healthcare provider.
- Be sure to subtract the dose already received. For example, if your dose is 0.6 mg and you can only set the dose selector to 0.3 mg, you should inject another 0.3 mg with a new Norditropin FlexPro pen.

Important:

- Never use the pen clicks to count the number of mg you select. Only the display window and pointer will show the exact number.
- Never use the growth hormone scale to measure how much liquid to inject. Only the display window and pointer will show the exact number.

Inject your dose

Make sure that you receive your full dose by using the injection technique recommended by your healthcare provider. This medicine is injected under your skin (subcutaneous) only.

H.

- Insert the needle into your skin as your healthcare provider has shown you.
- Press and hold the dose button to inject until the "0" in the display window lines up with the pointer. As you do this, you may hear or feel a firm click.
- If you remove your finger from the dose button before the “0” is in the display window the full dose has not been delivered. Leave the needle in the skin and press and hold the dose button again until the “0” lines up with the pointer.

If "0" does not appear in the display window, you did not receive the full dose. Call 1(-888-668-6444) for assistance.

- After the “0” in the display window lines up with the pointer, leave the needle under the skin for at least 6 seconds to make sure that you get your full dose. You can let go of the dose button while you wait.
- Change the injection site using the injection procedure recommended by your healthcare provider.

Important:

- Always press the dose button to inject the dose. Turning the dose selector will not inject the dose.
- Never touch the display window when you inject, as this can block the injection.

I.

- Remove the needle from your skin. After that, you may see a drop of liquid at the needle tip. This is normal and does not affect the dose you received.

- After the injection, remove the needle right away and put the pen cap back on. If the needle is not removed, some liquid may come out of the Norditropin FlexPro.
- Unscrew the needle and throw away the needle and any empty Norditropin FlexPro pen as directed by your healthcare provider. A special “sharps” container (such as a red biohazard container), a hard plastic container (such as an empty detergent bottle), or a metal container (such as an empty coffee can) should be used. The container should be sealed and disposed of properly.
- Caregivers should be most careful when handling used needles to avoid hurting themselves.

Care for your Norditropin FlexPro pen

You must take care of your Norditropin FlexPro pen:

- Do not drop your pen or knock it against hard surfaces. If you do drop it or think that something is wrong with it, always screw on a new disposable needle and check the growth hormone flow (airshot) before you inject.
- Do not try to refill your disposable pen – it is prefilled.
- Do not try to repair your pen or pull it apart.
- Do not expose your pen to dust, dirt or any kind of liquid.
- Do not try to wash, soak or lubricate your pen. You may clean the Norditropin FlexPro pen with a mild detergent on a moistened cloth. See section “How do I store Norditropin FlexPro?” above for information about how to store your pen.
- Always keep your pen and needles out of reach of others, especially children.
- Never share your needles and pen with anyone.

Date of Issue: March 2, 2010

Version: 1

US Patent Nos. 6,235,004; 6,004,297; 6,582,404; 6,716,198; 6,899,699; 5,849,704; 5,691,169; 5,618,697 and other patents pending.

Norditropin®, FlexPro®, Norditropin NordiFlex® and NordiFlex PenMate® are registered trademarks of Novo Nordisk Health Care AG.

Novo Nordisk® is a registered trademark of Novo Nordisk A/S.

© 2004-2010 Novo Nordisk Health Care AG

Manufactured by:

Novo Nordisk A/S

DK-2880 Bagsvaerd, Denmark

INSTRUCTIONS FOR USE

Norditropin® FlexPro®

(somatropin [rDNA origin] injection)

10 mg/1.5 mL (blue) Prefilled Pen

Read these instructions before using your Norditropin® FlexPro® pen.

Norditropin FlexPro contains 10 mg human growth hormone solution and delivers doses from 0.05 mg to 4 mg, in increments of 0.05 mg. Norditropin FlexPro is made to be used with Novo Nordisk® disposable needles. Needles are not included with Norditropin FlexPro.

Prepare your Norditropin FlexPro pen

A.

- Pull off the pen cap.
- Check that the liquid in the pen is clear and colorless by tipping it upside down 1 or 2 times. If the liquid looks unclear or cloudy, do not use the pen.
- Wash hands well and dry them.
- Wipe the front stopper on the needle thread with an alcohol swab.

B.

- Take a new disposable needle.
- Tear the paper tab off and screw the needle straight onto the pen.
- Make sure the needle is on tight.
- Never place a disposable needle on your Norditropin FlexPro pen until you are ready to give an injection.

C.

- Pull off the outer needle cap and inner needle cap and throw them both away.
- If you try to put the needle caps back on, you may accidentally hurt yourself with the needle.
- A drop of liquid may appear at the needle tip. This is normal.

Important:

- Always use a new needle for each injection. This will help prevent contamination.
- Never bend or damage the needle.

Check the growth hormone flow (airshot)

Make sure that you receive your full dose by checking the growth hormone flow (performing an airshot) before you select and inject your first dose from a new pen.

D. Turn the dose selector to select 0.05 mg. This is the smallest amount of medicine for a dose.

E.

- Hold the pen with the needle pointing up.
- Tap the top of the pen gently a few times to let any air bubbles rise to the top.

F.

- Press the dose button until the “0” in the display window lines up with the pointer and a drop of liquid appears at the needle tip.
- If no drop appears, repeat steps D, E, and F up to 6 times.
- If no drop appears after these attempts, change the needle and repeat steps D, E, and F one more time.
- If a drop of liquid still does not appear, call (1-888-668-6444) for help.

Important:

- Be careful not to drop Norditropin FlexPro pen or knock it against a hard surface. If this happens you will need to repeat the airshot.
- Always make sure that a drop appears at the needle tip after completing your airshot.

Select your dose

Use the dose selector on your Norditropin FlexPro pen to make sure you have the exact dose selected. You can select up to 4 mg per dose.

G.

- Select or adjust the dose you need by turning the dose selector forwards or backwards until the right number of mg lines up with the pointer.
- When dialing back, be careful not to press the dose button as liquid will come out.
- To guide you, the dose selector clicks differently when turned forwards, backwards or past the number of mg that is left in the pen.
- When the pen has less than 4 mg, the dose selector stops at the number of mg that is left in the pen.

How much growth hormone is left in the pen?

You can use the growth hormone scale to see how much growth hormone is left in the pen.

You can use the dose selector to see exactly how much growth hormone is left in the pen. If the pen contains less than 4 mg, turn the dose selector until it stops.

The figure that lines up with the pointer shows how many mg is left in the pen.

- You cannot set a dose higher than the number of mg left in the pen.
- If there is not enough Norditropin left in the pen to deliver your full dose, use a new Norditropin FlexPro pen to inject the remaining amount of your dose or contact your healthcare provider.
- Be sure to subtract the dose already received. For example, if your dose is 0.6 mg and you can only set the dose selector to 0.3 mg, you should inject another 0.3 mg with a new Norditropin FlexPro pen.

Important:

- Never use the pen clicks to count the number of mg you select. Only the display window and pointer will show the exact number.
- Never use the growth hormone scale to measure how much liquid to inject. Only the display window and pointer will show the exact number.

Inject your dose

Make sure that you receive your full dose by using the injection technique recommended by your healthcare provider. This medicine is injected under your skin (subcutaneous) only.

H.

- Insert the needle into your skin as your healthcare provider has shown you.
- Press and hold the dose button to inject until the “0” in the display window lines up with the pointer. As you do this, you may hear or feel a firm click.
- If you remove your finger from the dose button before the “0” is in the display window the full dose has not been delivered. Leave the needle in the skin and press and hold the dose button again until the “0” lines up with the pointer.

If “0” does not appear in the display window, you did not receive the full dose. Call (1-888-668-6444) for assistance.

- After the “0” in the display window lines up with the pointer, leave the needle under the skin for at least 6 seconds to make sure that you get your full dose. You can let go of the dose button while you wait.
- Change the injection site using the injection procedure recommended by your healthcare provider.

Important:

- Always press the dose button to inject the dose. Turning the dose selector will not inject the dose.
- Never touch the display window when you inject, as this can block the injection.

I.

- Remove the needle from your skin. After that, you may see a drop of liquid at the needle tip. This is normal and does not affect the dose you received.

- After the injection, remove the needle right away and put the pen cap back on. If the needle is not removed, some liquid may come out of the Norditropin FlexPro.
- Unscrew the needle and throw away the needle and any empty Norditropin FlexPro pen as directed by your healthcare provider. A special “sharps” container (such as a red biohazard container), a hard plastic container (such as an empty detergent bottle), or a metal container (such as an empty coffee can) should be used. The container should be sealed and disposed of properly.
- Caregivers should be most careful when handling used needles to avoid hurting themselves.

Care for your Norditropin FlexPro pen

You must take care of your Norditropin FlexPro pen:

- Do not drop your pen or knock it against hard surfaces. If you do drop it or think that something is wrong with it, always screw on a new disposable needle and check the growth hormone flow (airshot) before you inject.
- Do not try to refill your disposable pen – it is prefilled.
- Do not try to repair your pen or pull it apart.
- Do not expose your pen to dust, dirt or any kind of liquid.
- Do not try to wash, soak or lubricate your pen. You may clean the Norditropin FlexPro pen with a mild detergent on a moistened cloth. See section “How do I store Norditropin FlexPro?” above for information about how to store your pen.
- Always keep your pen and needles out of reach of others, especially children.
- Never share your needles and pen with anyone.

Date of Issue: March 2, 2010

Version: 1

US Patent Nos. 6,235,004; 6,004,297; 6,582,404; 6,716,198; 6,899,699; 5,849,704; 5,691,169; 5,618,697 and other patents pending.

Norditropin®, FlexPro®, Norditropin NordiFlex® and NordiFlex PenMate® are registered trademarks of Novo Nordisk Health Care AG.

Novo Nordisk® is a registered trademark of Novo Nordisk A/S.

© 2004-2010 Novo Nordisk Health Care AG

Manufactured by:

Novo Nordisk A/S

DK-2880 Bagsvaerd, Denmark

INSTRUCTIONS FOR USE

Norditropin® FlexPro®

(somatropin [rDNA origin] injection)

15 mg/1.5 mL (green) Prefilled Pen

Read these instructions before using your Norditropin® FlexPro® pen.

Norditropin FlexPro contains 15 mg human growth hormone solution and delivers doses from 0.1 mg to 8 mg, in increments of 0.1 mg. Norditropin FlexPro is made to be used with Novo Nordisk® disposable needles. Needles are not included with Norditropin FlexPro.

Prepare your Norditropin FlexPro pen

A.

- Pull off the pen cap.
- Check that the liquid in the pen is clear and colorless by tipping it upside down 1 or 2 times. If the liquid looks unclear or cloudy, do not use the pen.
- Wash hands well and dry them.
- Wipe the front stopper on the needle thread with an alcohol swab.

B.

- Take a new disposable needle.
- Tear the paper tab off and screw the needle straight onto the pen.
- Make sure the needle is on tight.
- Never place a disposable needle on your Norditropin FlexPro pen until you are ready to give an injection.

C.

- Pull off the outer needle cap and inner needle cap and throw them both away.
- If you try to put the needle caps back on, you may accidentally hurt yourself with the needle.
- A drop of liquid may appear at the needle tip. This is normal.

Important:

- Always use a new needle for each injection. This will help prevent contamination.
- Never bend or damage the needle.

Check the growth hormone flow (airshot)

Make sure that you receive your full dose by checking the growth hormone flow (performing an airshot) before you select and inject your first dose from a new pen.

D. Turn the dose selector to select 0.1 mg. This is the smallest amount of medicine for a dose.

E.

- Hold the pen with the needle pointing up.
- Tap the top of the pen gently a few times to let any air bubbles rise to the top.

F.

- Press the dose button until the “0” in the display window lines up with the pointer and a drop of liquid appears at the needle tip.
- If no drop appears, repeat steps D, E and F up to 6 times.
- If no drop appears after these attempts, change the needle and repeat steps D, E and F one more time.
- If a drop of liquid still does not appear, call (1-888-668-6444) for help.

Important:

- Be careful not to drop Norditropin FlexPro pen or knock it against a hard surface. If this happens you will need to repeat the airshot.
- Always make sure that a drop appears at the needle tip after completing your airshot.

Select your dose

Use the dose selector on your Norditropin FlexPro pen to make sure you have the exact dose selected. You can select up to 8 mg per dose.

G.

- Select or adjust the dose you need by turning the dose selector forwards or backwards until the right number of mg lines up with the pointer.
- When dialing back, be careful not to press the dose button as liquid will come out.
- To guide you, the dose selector clicks differently when turned forwards, backwards or past the number of mg that is left in the pen.
- When the pen has less than 8 mg, the dose selector stops at the number of mg that is left in the pen.

How much growth hormone is left in the pen?

You can use the growth hormone scale to see how much growth hormone is left in the pen.

You can use the dose selector to see exactly how much growth hormone is left in the pen. If the pen contains less than 8 mg, turn the dose selector until it stops.

The figure that lines up with the pointer shows how many mg is left in the pen.

- You cannot set a dose higher than the number of mg left in the pen.
- If there is not enough Norditropin left in the pen to deliver your full dose, use a new Norditropin FlexPro pen to inject the remaining amount of your dose or contact your healthcare provider.
- Be sure to subtract the dose already received. For example, if your dose is 0.6 mg and you can only set the dose selector to 0.3 mg, you should inject another 0.3 mg with a new Norditropin FlexPro pen.

Important:

- Never use the pen clicks to count the number of mg you select. Only the display window and pointer will show the exact number.
- Never use the growth hormone scale to measure how much liquid to inject. Only the display window and pointer will show the exact number.

Inject your dose

Make sure that you receive your full dose by using the injection technique recommended by your healthcare provider. This medicine is injected under your skin (subcutaneous) only.

H.

- Insert the needle into your skin as your healthcare provider has shown you.
- Press and hold the dose button to inject until the “0” in the display window lines up with the pointer. As you do this, you may hear or feel a firm click.
- If you remove your finger from the dose button before the “0” is in the display window the full dose has not been delivered. Leave the needle in the skin and press and hold the dose button again until the “0” lines up with the pointer.

If “0” does not appear in the display window, you did not receive the full dose. Call (1-888-668-6444) for assistance.

- After the “0” in the display window lines up with the pointer, leave the needle under the skin for at least 6 seconds to make sure that you get your full dose. You can let go of the dose button while you wait.

- Change the injection site using the injection procedure recommended by your healthcare provider.

Important:

- Always press the dose button to inject the dose. Turning the dose selector will not inject the dose.
- Never touch the display window when you inject, as this can block the injection.

I.

- Remove the needle from your skin. After that, you may see a drop of liquid at the needle tip. This is normal and does not affect the dose you received.

- After the injection, remove the needle right away and put the pen cap back on. If the needle is not removed, some liquid may come out of the Norditropin FlexPro.
- Unscrew the needle and throw away the needle and any empty Norditropin FlexPro pen as directed by your healthcare provider. A special “sharps” container (such as a red biohazard container), a hard plastic container (such as an empty detergent bottle), or a metal container (such as an empty coffee can) should be used. The container should be sealed and disposed of properly.
- Caregivers should be most careful when handling used needles to avoid hurting themselves.

Care for your Norditropin FlexPro pen

You must take care of your Norditropin FlexPro pen:

- Do not drop your pen or knock it against hard surfaces. If you do drop it or think that something is wrong with it, always screw on a new disposable needle and check the growth hormone flow (airshot) before you inject.
- Do not try to refill your disposable pen – it is prefilled.
- Do not try to repair your pen or pull it apart.
- Do not expose your pen to dust, dirt or any kind of liquid.
- Do not try to wash, soak or lubricate your pen. You may clean the Norditropin FlexPro pen with a mild detergent on a moistened cloth. See section “How do I store Norditropin FlexPro?” above for information about how to store your pen.
- Always keep your pen and needles out of reach of others, especially children.
- Never share your needles and pen with anyone.

Date of Issue: March 2, 2010

Version: 1

US Patent Nos. 6,235,004; 6,004,297; 6,582,404; 6,716,198; 6,899,699; 5,849,704; 5,691,169; 5,618,697 and other patents pending.

Norditropin®, FlexPro®, Norditropin NordiFlex® and NordiFlex PenMate® are registered trademarks of Novo Nordisk Health Care AG.

Novo Nordisk® is a registered trademark of Novo Nordisk A/S.

© 2004-2010 Novo Nordisk Health Care AG

Manufactured by:

Novo Nordisk A/S

DK-2880 Bagsvaerd, Denmark

PRINCIPAL DISPLAY PANEL - NORDITROPIN NORDIFLEX 5 MG/1.5ML

Norditropin NordiFlex®

Somatropin (rDNA origin) injection

5 mg/1.5 mL Prefilled Pen

1 x 1.5 mL prefilled disposable pen

Each 1.5 mL contains 5 mg somatropin

CONTAINS ONE

NORDITROPIN NORDIFLEX® 5 mg/1.5 mL

Rx ONLY

List: 770411

Before use MUST keep refrigerated. (2ºC-8ºC/36ºF-46ºF). Do not store with needles. After initial injection, EITHER keep refrigerated for 4 weeks OR store not above 25ºC (77ºF) for 3 weeks. Do not freeze. Discard unused portion. Avoid direct light. Keep out of the reach and sight of children. For subcutaneous administration only. Please read the enclosed leaflet before use.